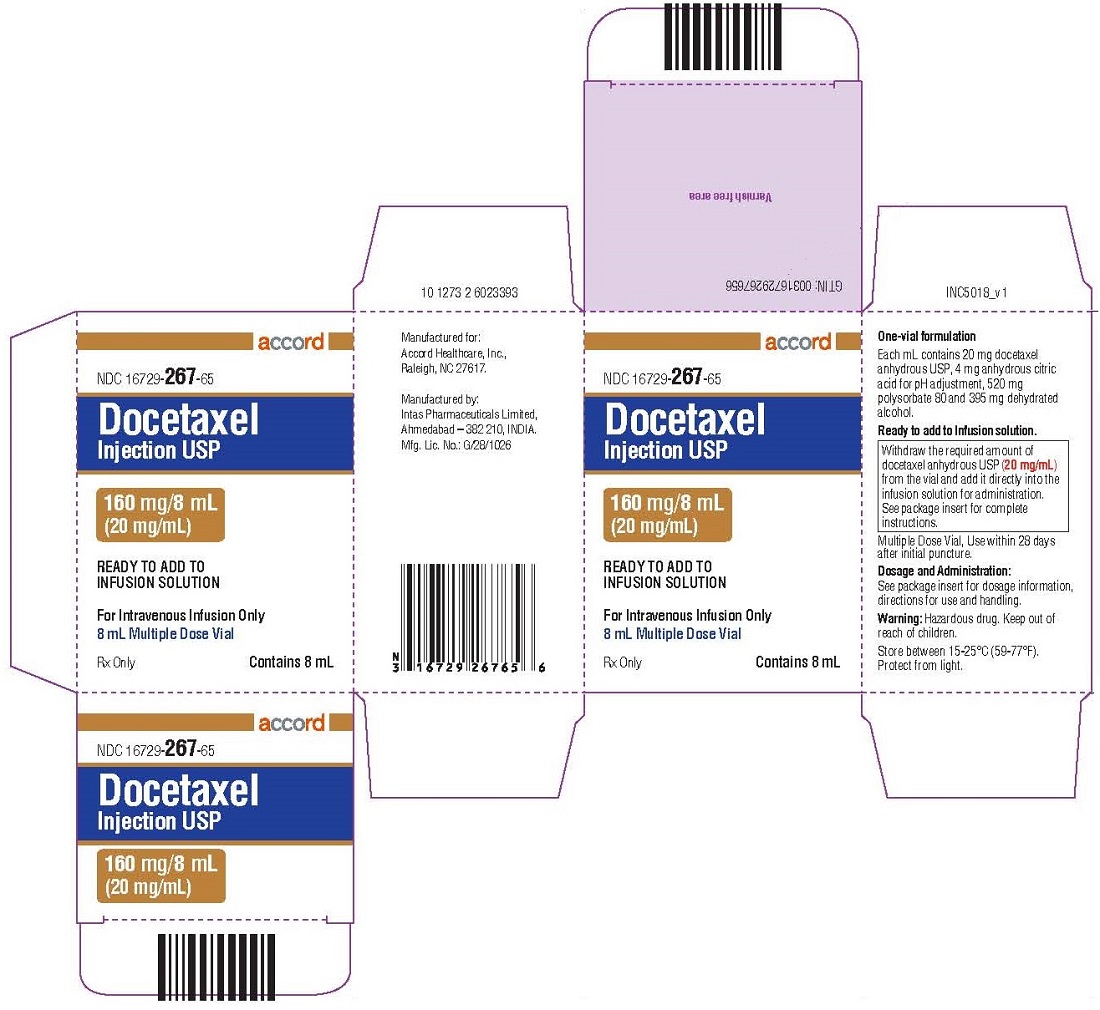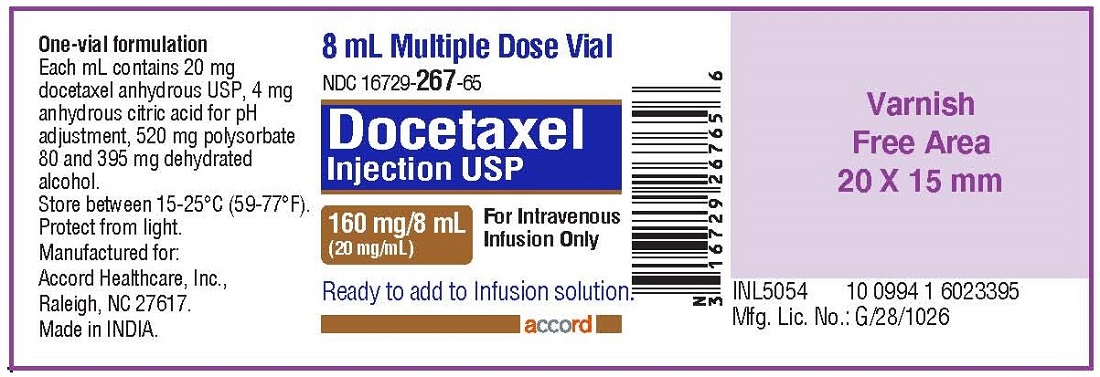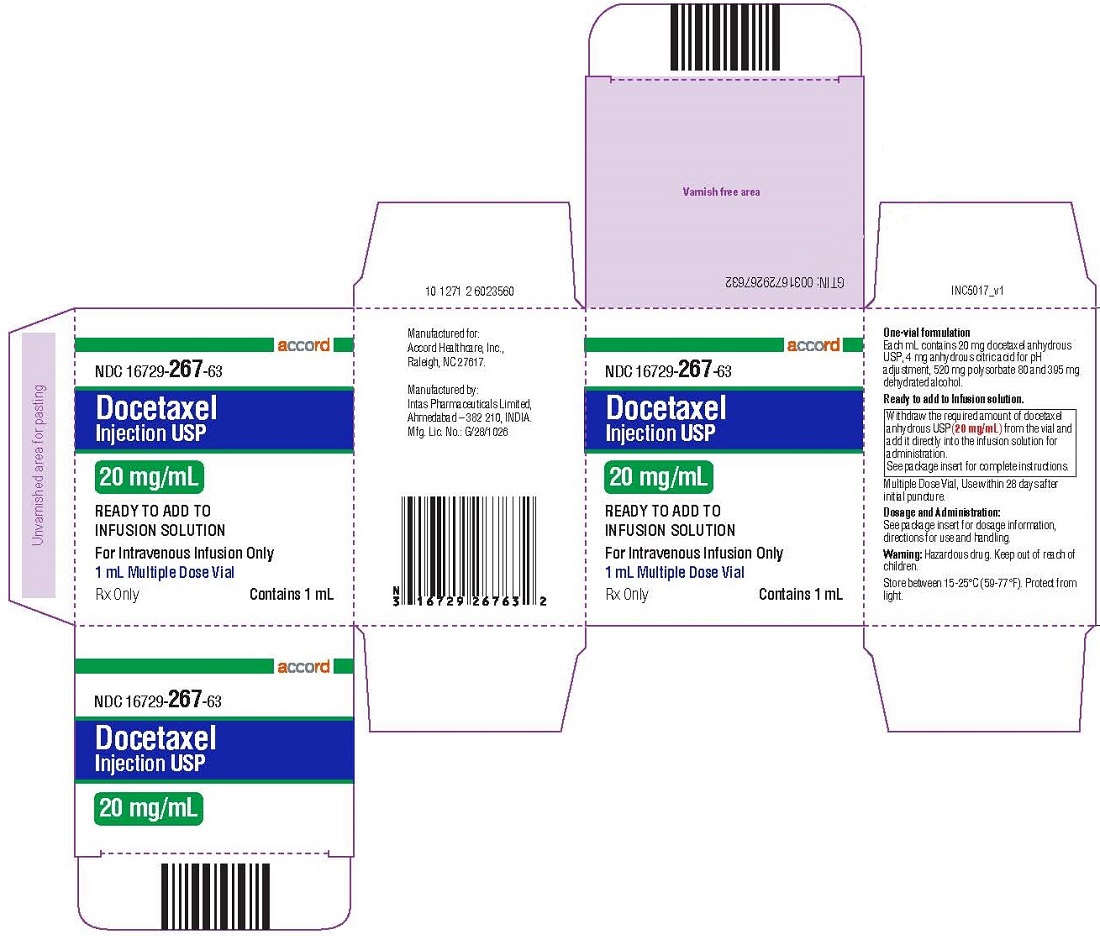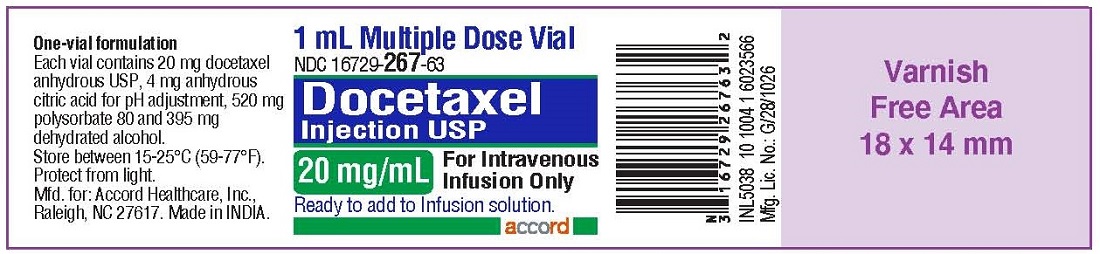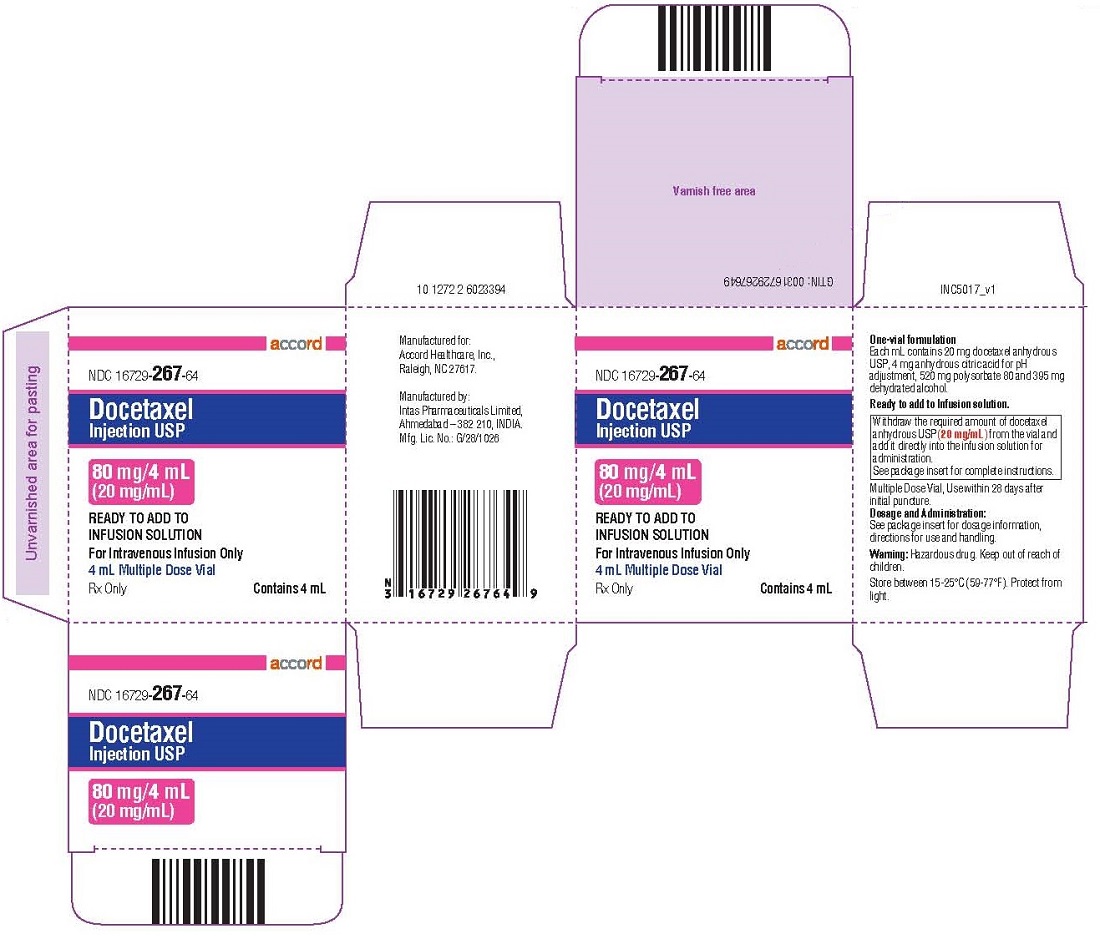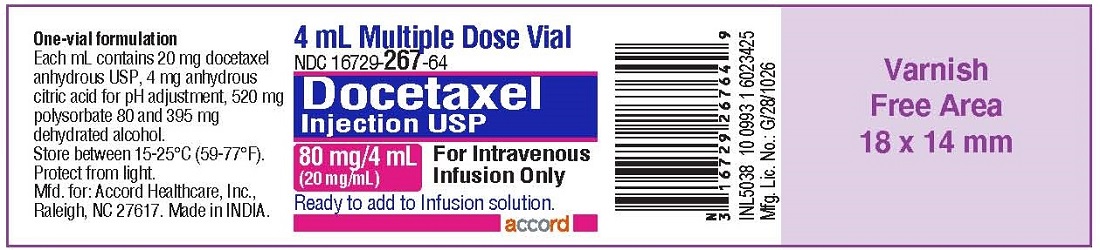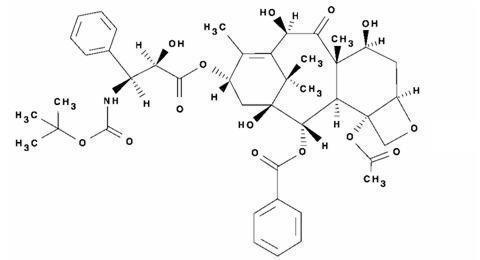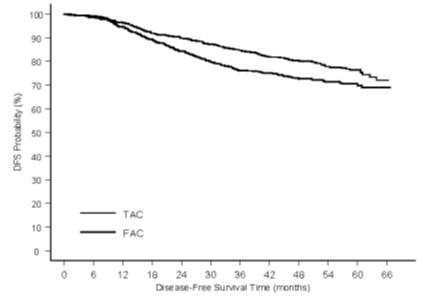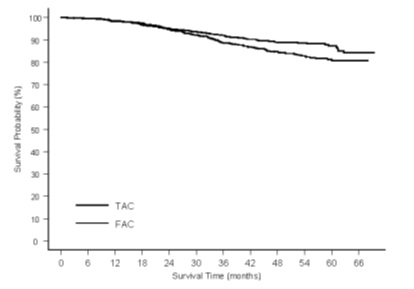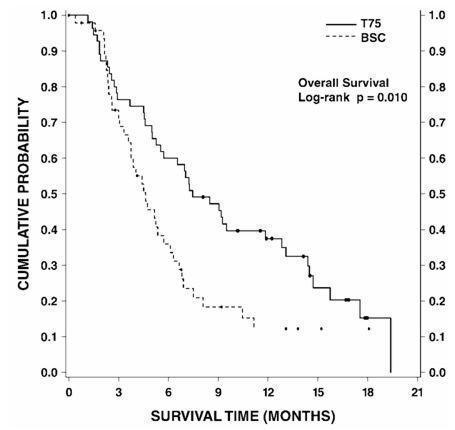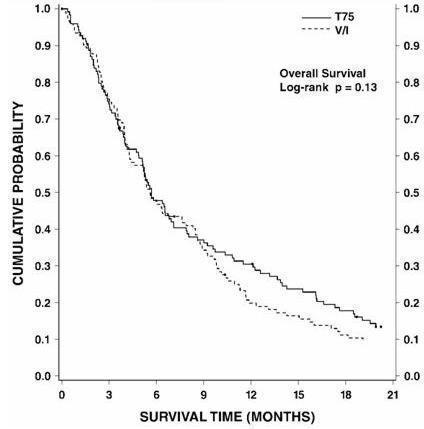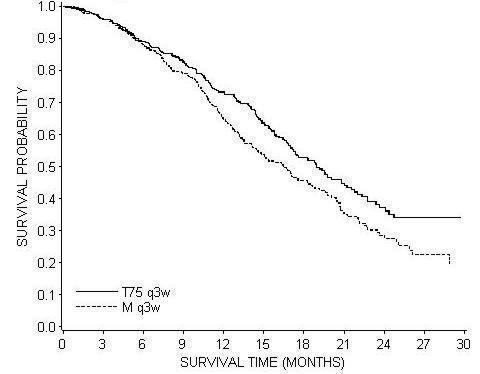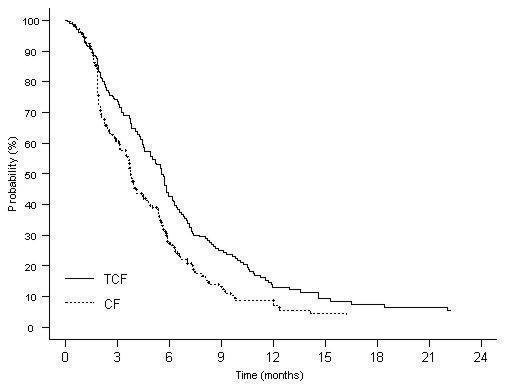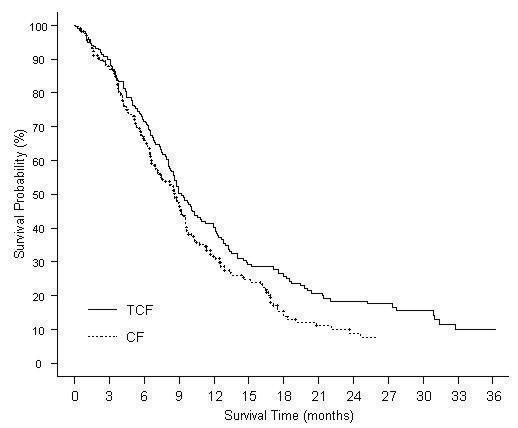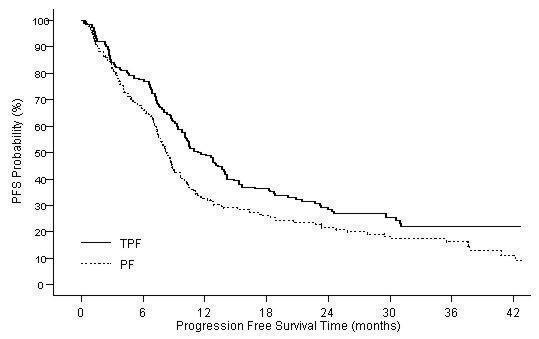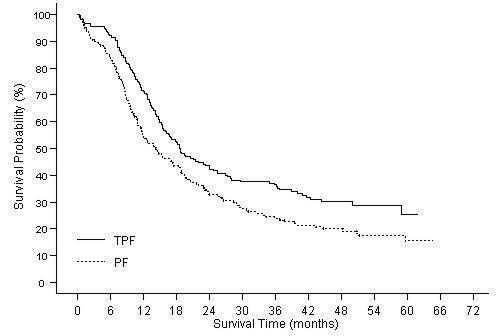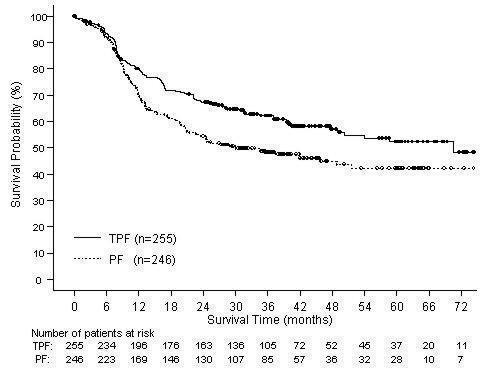 DRUG LABEL: DOCETAXEL
NDC: 16729-231 | Form: INJECTION, SOLUTION, CONCENTRATE
Manufacturer: Accord Healthcare Inc.
Category: prescription | Type: HUMAN PRESCRIPTION DRUG LABEL
Date: 20240815

ACTIVE INGREDIENTS: DOCETAXEL ANHYDROUS 20 mg/1 mL
INACTIVE INGREDIENTS: ANHYDROUS CITRIC ACID 4 mg/1 mL; POLYSORBATE 80 520 mg/1 mL; ALCOHOL 395 mg/1 mL

HIGHLIGHTS OF PRESCRIBING INFORMATION

These highlights do not include all the information needed to use DOCETAXEL INJECTION safely and effectively. See full prescribing information for DOCETAXEL INJECTION.
DOCETAXEL injection, for intravenous use
Initial U.S. Approval: 1996

WARNING: TOXIC DEATHS, HEPATOTOXICITY, NEUTROPENIA, HYPERSENSITIVITY REACTIONS, and FLUID RETENTION

See full prescribing information for complete boxed warning.

- Treatment-related mortality increases with abnormal liver function, at higher doses, and in patients with NSCLC and prior platinum-based therapy receiving Docetaxel Injection at 100 mg/m^2(5.1)
- Avoid use of Docetaxel Injection if bilirubin > ULN, or if AST and/or ALT >1.5 × ULN concomitant with alkaline phosphatase >2.5 × ULN. LFT elevations increase risk of severe or life-threatening complications. Obtain LFTs before each treatment cycle (5.2)
- Do not administer Docetaxel Injection to patients with neutrophil counts <1500 cells/mm^3. Obtain frequent blood counts to monitor for neutropenia (4, 5.3)
- Severe hypersensitivity, including fatal anaphylaxis, has been reported in patients who received dexamethasone premedication. Severe reactions require immediate discontinuation of Docetaxel Injection and administration of appropriate therapy (5.5)
- Contraindicated if history of severe hypersensitivity reactions to Docetaxel Injection or to drugs formulated with polysorbate 80 (4)
- Severe fluid retention may occur despite dexamethasone (5.6)

1 INDICATIONS AND USAGE

Docetaxel Injection is a microtubule inhibitor indicated for:

- Breast Cancer (BC): single agent for locally advanced or metastatic BC after chemotherapy failure; and with doxorubicin and cyclophosphamide as adjuvant treatment of operable node-positive BC (1.1)
- Non-small Cell Lung Cancer (NSCLC): single agent for locally advanced or metastatic NSCLC after platinum therapy failure; and with cisplatin for unresectable, locally advanced or metastatic untreated NSCLC (1.2)
- Castration-Resistant Prostate Cancer (CRPC): with prednisone in metastatic castration-resistant prostate cancer (1.3)
- Gastric Adenocarcinoma (GC): with cisplatin and fluorouracil for untreated, advanced GC, including the gastroesophageal junction (1.4)
- Squamous Cell Carcinoma of the Head and Neck (SCCHN): with cisplatin and fluorouracil for induction treatment of locally advanced SCCHN (1.5)

2 DOSAGE AND ADMINISTRATION

Administer in a facility equipped to manage possible complications (e.g., anaphylaxis).Administer intravenously (IV) over 1 hr every 3 weeks. PVC equipment is not recommended. Use only a 21 gauge needle to withdraw Docetaxel Injection from the vial.

- BC locally advanced or metastatic: 60 mg/m^2to 100 mg/m^2single agent (2.1)
- BC adjuvant: 75 mg/m^2administered 1 hour after doxorubicin 50 mg/m^2and cyclophosphamide 500 mg/m^2every 3 weeks for 6 cycles (2.1)
- NSCLC: after platinum therapy failure: 75 mg/m^2single agent (2.2)
- NSCLC: chemotherapy naive: 75 mg/m^2followed by cisplatin 75 mg/m^2(2.2)
- HRPC: 75 mg/m^2with 5 mg prednisone twice a day continuously (2.3)
- GC: 75 mg/m^2followed by cisplatin 75 mg/m^2(both on day 1 only) followed by fluorouracil 750 mg/m^2per day as a 24-hr IV (days 1-5), starting at end of cisplatin infusion (2.4)
- SCCHN: 75 mg/m^2followed by cisplatin 75 mg/m^2IV (day 1), followed by fluorouracil 750 mg/m^2per day as a 24-hr IV (days 1-5), starting at end of cisplatin infusion; for 4 cycles (2.5)
- SCCHN: 75 mg/m^2followed by cisplatin 100 mg/m^2IV (day 1), followed by fluorouracil 1000 mg/m^2per day as a 24-hr IV (days 1-4); for 3 cycles (2.5)

For all patients:

- Premedicate with oral corticosteroids (2.6)
- Adjust dose as needed (2.7)

3 DOSAGE FORMS AND STRENGTHS

- Injection: One vial Docetaxel Injection: Multiple dose vials
  160 mg/8 mL, 80 mg/4 mL and 20 mg/mL (3)

4 CONTRAINDICATIONS

- Hypersensitivity to docetaxel or polysorbate 80 (4)
- Neutrophil counts of <1500 cells/mm^3(4)

5 WARNINGS AND PRECAUTIONS

- Second primary malignancies: In patients treated with Docetaxel Injection-containing regimens, monitor for delayed AML, MDS, NHL, and renal cancer. (5.7)
- Cutaneous reactions: Reactions including erythema of the extremities with edema followed by desquamation may occur. Severe cutaneous adverse reactions have been reported. Severe skin toxicity may require dose adjustment or permanent treatment discontinuation. (5.8)
- Neurologic reactions: Reactions including paresthesia, dysesthesia, and pain may occur. Severe neurosensory symptoms require dose adjustment or discontinuation if persistent. (5.9)
- Eye disorders: Cystoid macular edema (CME) has been reported and requires treatment discontinuation. (5.10)
- Asthenia: Severe asthenia may occur and may require treatment discontinuation. (5.11)
- Embryo-fetal toxicity: Can cause fetal harm. Advise patients of the potential risk to a fetus and to use effective contraception. (5.12, 8.1, 8.3)
- Alcohol content: The alcohol content in a dose of Docetaxel Injection may affect the central nervous system. This may include impairment of a patient’s ability to drive or use machines immediately after infusion. (5.13)
- Tumor lysis syndrome: Tumor lysis syndrome has been reported. Patients at risk should be well hydrated and closely monitored during treatment. (5.14)

6 ADVERSE REACTIONS

Most common adverse reactions across all Docetaxel Injection indications are infections, neutropenia, anemia, febrile neutropenia, hypersensitivity, thrombocytopenia, neuropathy, dysgeusia, dyspnea, constipation, anorexia, nail disorders, fluid retention, asthenia, pain, nausea, diarrhea, vomiting, mucositis, alopecia, skin reactions, and myalgia. (6)

To report SUSPECTED ADVERSE REACTIONS, contact Accord Healthcare Inc. at 1866-941-7875 or FDA at 1-800-FDA-1088 or www.fda.gov/medwatch.

7 DRUG INTERACTIONS

- Cytochrome P450 3A4 inducers, inhibitors, or substrates: May alter docetaxel metabolism. (7)

8 USE IN SPECIFIC POPULATIONS

- Lactation: Advise women not to breastfeed. (8.2)
- Females and Males of Reproductive Potential: Verify pregnancy status of females prior to initiation of Docetaxel Injection. (8.3)

FULL PRESCRIBING INFORMATION

WARNING: TOXIC DEATHS, HEPATOTOXICITY, NEUTROPENIA, HYPERSENSITIVITY REACTIONS, and FLUID RETENTION

Treatment-related mortality associated with Docetaxel Injection is increased in patients with abnormal liver function, in patients receiving higher doses, and in patients with non-small cell lung carcinoma and a history of prior treatment with platinum-based chemotherapy who receive Docetaxel Injection as a single agent at a dose of 100 mg/m^2 [see Warnings and Precautions (5.1)].

Avoid the use of Docetaxel Injection in patients with bilirubin > upper limit of normal (ULN), or to patients with AST and/or ALT >1.5 × ULN concomitant with alkaline phosphatase >2.5 × ULN. Patients with elevations of bilirubin or abnormalities of transaminase concurrent with alkaline phosphatase are at increased risk for the development of severe neutropenia, febrile neutropenia, infections, severe thrombocytopenia, severe stomatitis, severe skin toxicity, and toxic death. Patients with isolated elevations of transaminase >1.5 × ULN also had a higher rate of febrile neutropenia. Measure bilirubin, AST or ALT, and alkaline phosphatase prior to each cycle of Docetaxel Injection [see Warnings and Precautions (5.2)].

Do not administer Docetaxel Injection to patients with neutrophil counts of <1500 cells/mm^3. Monitor blood counts frequently as neutropenia may be severe and result in infection [see Warnings and Precautions (5.3)].

Do not administer Docetaxel Injection to patients who have a history of severe hypersensitivity reactions to Docetaxel Injection or to other drugs formulated with polysorbate 80 [see Contraindications (4)] . Severe hypersensitivity reactions have been reported in patients despite dexamethasone premedication. Hypersensitivity reactions require immediate discontinuation of the Docetaxel Injection infusion and administration of appropriate therapy [see Warnings and Precautions (5.5)] .

Severe fluid retention occurred in 6.5% (6/92) of patients despite use of dexamethasone premedication. It was characterized by one or more of the following events: poorly tolerated peripheral edema, generalized edema, pleural effusion requiring urgent drainage, dyspnea at rest, cardiac tamponade, or pronounced abdominal distention (due to ascites) [see Warnings and Precautions (5.6)].

1 INDICATIONS AND USAGE

1.1 Breast Cancer

Docetaxel Injection is indicated for the treatment of patients with locally advanced or metastatic breast cancer after failure of prior chemotherapy.

Docetaxel Injection in combination with doxorubicin and cyclophosphamide is indicated for the adjuvant treatment of patients with operable node-positive breast cancer.

1.2 Non-small Cell Lung Cancer

Docetaxel Injection as a single agent is indicated for the treatment of patients with locally advanced or metastatic non-small cell lung cancer after failure of prior platinum-based chemotherapy.

Docetaxel Injection in combination with cisplatin is indicated for the treatment of patients with unresectable, locally advanced or metastatic non-small cell lung cancer who have not previously received chemotherapy for this condition.

1.3 Prostate Cancer

Docetaxel Injection in combination with prednisone is indicated for the treatment of patients with metastatic castration-resistant prostate cancer.

1.4 Gastric Adenocarcinoma

Docetaxel Injection in combination with cisplatin and fluorouracil is indicated for the treatment of patients with advanced gastric adenocarcinoma, including adenocarcinoma of the gastroesophageal junction, who have not received prior chemotherapy for advanced disease.

1.5 Head and Neck Cancer

Docetaxel Injection in combination with cisplatin and fluorouracil is indicated for the induction treatment of patients with locally advanced squamous cell carcinoma of the head and neck (SCCHN).

2 DOSAGE AND ADMINISTRATION

For all indications, toxicities may warrant dosage adjustments [see Dosage and Administration (2.7)].

Administer in a facility equipped to manage possible complications (e.g. anaphylaxis).

2.1 Breast Cancer

- For locally advanced or metastatic breast cancer after failure of prior chemotherapy, the recommended dose of Docetaxel Injection is 60 mg/m^2to 100 mg/m^2administered intravenously over 1 hour every 3 weeks.
- For the adjuvant treatment of operable node-positive breast cancer, the recommended Docetaxel Injection dose is 75 mg/m^2administered 1 hour after doxorubicin 50 mg/m^2and cyclophosphamide 500 mg/m^2every 3 weeks for 6 courses. Prophylactic G-CSF may be used to mitigate the risk of hematological toxicities [see Dosage and Administration (2.7)].

2.2 Non-small Cell Lung Cancer

- For treatment after failure of prior platinum-based chemotherapy, Docetaxel Injection was evaluated as monotherapy, and the recommended dose is 75 mg/m^2administered intravenously over 1 hour every 3 weeks. A dose of 100 mg/m^2in patients previously treated with chemotherapy was associated with increased hematologic toxicity, infection, and treatment-related mortality in randomized controlled trials [see Boxed Warning, Dosage and Administration (2.7), Warnings and Precautions (5), Clinical Studies (14)] .
- For chemotherapy-naive patients, Docetaxel Injection was evaluated in combination with cisplatin.
  The recommended dose of Docetaxel Injection is 75 mg/m^2administered intravenously over 1 hour immediately followed by cisplatin 75 mg/m^2over 30-60 minutes every 3 weeks [see Dosage and Administration (2.7)] .

2.3 Prostate Cancer

- For metastatic castration-resistant prostate cancer, the recommended dose of Docetaxel Injection is 75 mg/m^2every 3 weeks as a 1 hour intravenous infusion. Prednisone 5 mg orally twice daily is administered continuously [see Dosage and Administration (2.7)] .

2.4 Gastric Adenocarcinoma

- For gastric adenocarcinoma, the recommended dose of Docetaxel Injection is 75 mg/m^2as a 1 hour intravenous infusion, followed by cisplatin 75 mg/m^2, as a 1 to 3 hour intravenous infusion (both on day 1 only), followed by fluorouracil 750 mg/m^2per day given as a 24-hour continuous intravenous infusion for 5 days, starting at the end of the cisplatin infusion. Treatment is repeated every three weeks. Patients must receive premedication with antiemetics and appropriate hydration for cisplatin administration [see Dosage and Administration (2.7)] .

2.5 Head and Neck Cancer

Patients must receive premedication with antiemetics, and appropriate hydration (prior to and after cisplatin administration). Prophylaxis for neutropenic infections should be administered. All patients treated on the Docetaxel Injection containing arms of the TAX323 and TAX324 studies received prophylactic antibiotics.

- Induction Chemotherapy Followed by Radiotherapy (TAX323)
  For the induction treatment of locally advanced inoperable SCCHN, the recommended dose of Docetaxel Injection is 75 mg/m^2as a 1 hour intravenous infusion followed by cisplatin 75 mg/m^2intravenously over 1 hour, on day one, followed by fluorouracil as a continuous intravenous infusion at 750 mg/m^2per day for five days. This regimen is administered every 3 weeks for 4 cycles. Following chemotherapy, patients should receive radiotherapy [see Dosage and Administration (2.7)] .

- Induction Chemotherapy Followed by Chemoradiotherapy (TAX324)
  For the induction treatment of patients with locally advanced (unresectable, low surgical cure, or organ preservation) SCCHN, the recommended dose of Docetaxel Injection is 75 mg/m^2as a 1 hour intravenous infusion on day 1, followed by cisplatin 100 mg/m^2administered as a 30-minute to 3 hour infusion, followed by fluorouracil 1000 mg/m^2/day as a continuous infusion from day 1 to day 4. This regimen is administered every 3 weeks for 3 cycles. Following chemotherapy, patients should receive chemoradiotherapy [see Dosage and Administration (2.7)] .

2.6 Premedication Regimen

All patients should be premedicated with oral corticosteroids (see below for prostate cancer) such as dexamethasone 16 mg per day (e.g., 8 mg twice daily) for 3 days starting 1 day prior to Docetaxel Injection administration in order to reduce the incidence and severity of fluid retention as well as the severity of hypersensitivity reactions [see Boxed Warning, Warnings and Precautions (5.5)] .

For metastatic castration-resistant prostate cancer, given the concurrent use of prednisone, the recommended premedication regimen is oral dexamethasone 8 mg at 12 hours, 3 hours, and 1 hour before the Docetaxel Injection infusion [see Warnings and Precautions (5.5)] .

2.7 Dosage Adjustments during Treatment

Breast Cancer

Patients who are dosed initially at 100 mg/m^2and who experience either febrile neutropenia, neutrophils <500 cells/mm^3for more than 1 week, or severe or cumulative cutaneous reactions during Docetaxel Injection therapy should have the dosage adjusted from 100 mg/m^2to 75 mg/m^2. If the patient continues to experience these reactions, the dosage should either be decreased from 75 mg/m^2to 55 mg/m^2or the treatment should be discontinued. Conversely, patients who are dosed initially at 60 mg/m^2and who do not experience febrile neutropenia, neutrophils <500 cells/mm^3for more than 1 week, severe or cumulative cutaneous reactions, or severe peripheral neuropathy during Docetaxel Injection therapy may tolerate higher doses. Patients who develop ≥grade 3 peripheral neuropathy should have Docetaxel Injection treatment discontinued entirely.

Combination Therapy with Docetaxel Injection in the Adjuvant Treatment of Breast Cancer

Docetaxel Injection in combination with doxorubicin and cyclophosphamide should be administered when the neutrophil count is ≥1,500 cells/mm^3. Patients who experience febrile neutropenia should receive G-CSF in all subsequent cycles. Patients who continue to experience this reaction should remain on G-CSF and have their Docetaxel Injection dose reduced to 60 mg/m^2. Patients who experience grade 3 or 4 stomatitis should have their Docetaxel Injection dose decreased to 60 mg/m^2. Patients who experience severe or cumulative cutaneous reactions or moderate neurosensory signs and/or symptoms during Docetaxel Injection therapy should have their dosage of Docetaxel Injection reduced from 75 mg/m^2to 60 mg/m^2. If the patient continues to experience these reactions at 60 mg/m^2, treatment should be discontinued.

Non-small Cell Lung Cancer

Monotherapy with Docetaxel Injection for NSCLC treatment after failure of prior platinum-based chemotherapy

Patients who are dosed initially at 75 mg/m^2and who experience either febrile neutropenia, neutrophils <500 cells/mm^3for more than one week, severe or cumulative cutaneous reactions, or other grade 3/4 non-hematological toxicities during Docetaxel Injection treatment should have treatment withheld until resolution of the toxicity and then resumed at 55 mg/m^2. Patients who develop ≥grade 3 peripheral neuropathy should have Docetaxel Injection treatment discontinued entirely.

Combination therapy with Docetaxel Injection for chemotherapy-naive NSCLC

For patients who are dosed initially at Docetaxel Injection 75 mg/m^2in combination with cisplatin, and whose nadir of platelet count during the previous course of therapy is <25,000 cells/mm^3, in patients who experience febrile neutropenia, and in patients with serious non-hematologic toxicities, the Docetaxel Injection dosage in subsequent cycles should be reduced to 65 mg/m^2. In patients who require a further dose reduction, a dose of 50 mg/m^2is recommended. For cisplatin dosage adjustments, see manufacturers' prescribing information.

Prostate Cancer

Combination therapy with Docetaxel Injection for metastatic castration-resistant prostate cancer

Docetaxel Injection should be administered when the neutrophil count is ≥1,500 cells/mm^3. Patients who experience either febrile neutropenia, neutrophils <500 cells/mm^3for more than one week, severe or cumulative cutaneous reactions or moderate neurosensory signs and/or symptoms during Docetaxel Injection therapy should have the dosage of Docetaxel Injection reduced from 75 mg/m^2to 60 mg/m^2. If the patient continues to experience these reactions at 60 mg/m^2, the treatment should be discontinued.

Gastric or Head and Neck Cancer

Docetaxel Injection in combination with cisplatin and fluorouracil in gastric cancer or head and neck cancer

Patients treated with Docetaxel Injection in combination with cisplatin and fluorouracil must receive antiemetics and appropriate hydration according to current institutional guidelines. In both studies, G-CSF was recommended during the second and/or subsequent cycles in case of febrile neutropenia, or documented infection with neutropenia, or neutropenia lasting more than 7 days. If an episode of febrile neutropenia, prolonged neutropenia or neutropenic infection occurs despite G-CSF use, the Docetaxel Injection dose should be reduced from 75 mg/m^2to 60 mg/m^2. If subsequent episodes of complicated neutropenia occur the Docetaxel Injection dose should be reduced from 60 mg/m^2to 45 mg/m^2. In case of grade 4 thrombocytopenia the Docetaxel Injection dose should be reduced from 75 mg/m^2to 60 mg/m^2. Do not retreat patients with subsequent cycles of Docetaxel Injection until neutrophils recover to a level >1,500 cells/mm^3 [see Contraindications (4)]. Avoid retreating patients until platelets recover to a level >100,000 cells/mm^3. Discontinue treatment if these toxicities persist [see Warnings and Precautions (5.3)].

Recommended dose modifications for toxicities in patients treated with Docetaxel Injection in combination with cisplatin and fluorouracil are shown in Table 1.

Table 1 : Recommended Dose Modifications for Toxicities in Patients Treated with Docetaxel Injection in Combination with Cisplatin and Fluorouracil
Toxicity | Dosage adjustment
Diarrhea grade 3 | First episode: reduce fluorouracil dose by 20%. Second episode: then reduce Docetaxel Injection dose by 20%.
Diarrhea grade 4 | First episode: reduce Docetaxel Injection and fluorouracil doses by 20%. Second episode: discontinue treatment.
Stomatitis/mucositis grade 3 | First episode: reduce fluorouracil dose by 20%. Second episode: stop fluorouracil only, at all subsequent cycles. Third episode: reduce Docetaxel Injection dose by 20%.
Stomatitis/mucositis grade 4 | First episode: stop fluorouracil only, at all subsequent cycles. Second episode: reduce Docetaxel Injection dose by 20%.

Liver dysfunction:

In case of AST/ALT >2.5 to ≤5 × ULN and AP ≤2.5 × ULN, or AST/ALT >1.5 to ≤5 × ULN and AP >2.5 to ≤5 × ULN, Docetaxel Injection should be reduced by 20%.

In case of AST/ALT >5 × ULN and/or AP >5 × ULN Docetaxel Injection should be stopped.

The dose modifications for cisplatin and fluorouracil in the gastric cancer study are provided below.

Cisplatin dose modifications and delays

Peripheral neuropathy: A neurological examination should be performed before entry into the study, and then at least every 2 cycles and at the end of treatment. In the case of neurological signs or symptoms, more frequent examinations should be performed and the following dose modifications can be made according to NCI-CTCAE grade:

• Grade 2: Reduce cisplatin dose by 20%.

• Grade 3: Discontinue treatment.

Ototoxicity: In the case of grade 3 toxicity, discontinue treatment.

Nephrotoxicity: In the event of a rise in serum creatinine ≥grade 2 (>1.5 × normal value) despite adequate rehydration, CrCl should be determined before each subsequent cycle and the following dose reductions should be considered (see Table 2).

For other cisplatin dosage adjustments, also refer to the manufacturers’ prescribing information.

Table 2 : Dose Reductions for Evaluation of Creatinine Clearance
Creatinine clearance result before next cycle | Cisplatin dose next cycle
CrCl ≥60 mL/min | Full dose of cisplatin was given. CrCl was to be repeated before each treatment cycle.
 | Dose of cisplatin was reduced by 50% at subsequent cycle. If CrCl was >60 mL/min at end of cycle, full cisplatin dose was reinstituted at the next cycle.
CrCl between 40 and 59 mL/min
 | If no recovery was observed, then cisplatin was omitted from the next treatment cycle.
 | Dose of cisplatin was omitted in that treatment cycle only.
 | If CrCl was still <40 mL/min at the end of cycle, cisplatin was discontinued.
CrCl <40 mL/min
 | If CrCl was >40 and <60 mL/min at end of cycle, a 50% cisplatin dose was given at the next cycle.
 | If CrCl was >60 mL/min at end of cycle, full cisplatin dose was given at next cycle.
CrCl = Creatinine clearance

Fluorouracil dose modifications and treatment delays

For diarrhea and stomatitis, see Table 1.

In the event of grade 2 or greater plantar-palmar toxicity, fluorouracil should be stopped until recovery. The fluorouracil dosage should be reduced by 20%.

For other greater than grade 3 toxicities, except alopecia and anemia, chemotherapy should be delayed (for a maximum of 2 weeks from the planned date of infusion) until resolution to grade ≤1 and then recommenced, if medically appropriate.

For other fluorouracil dosage adjustments, also refer to the manufacturers’ prescribing information.

Combination Therapy with Strong CYP3A4 Inhibitors

Avoid using concomitant strong CYP3A4 inhibitors (e.g., ketoconazole, itraconazole, clarithromycin, atazanavir, indinavir, nefazodone, nelfinavir, ritonavir, saquinavir, telithromycin and voriconazole). There are no clinical data with a dose adjustment in patients receiving strong CYP3A4 inhibitors. Based on extrapolation from a pharmacokinetic study with ketoconazole in 7 patients, consider a 50% docetaxel dose reduction if patients require coadministration of a strong CYP3A4 inhibitor [see Drug Interactions (7), Clinical Pharmacology (12.3)].

2.8 Administration Precautions

Docetaxel Injection is a hazardous anticancer drug and, as with other potentially toxic compounds, caution should be exercised when handling and preparing Docetaxel Injection solutions. The use of gloves is recommended [ see How Supplied/Storage and Handling (16.3)] .

If Docetaxel Injection initial diluted solution, or final dilution for infusion should come into contact with the skin, immediately and thoroughly wash with soap and water. If Docetaxel Injection initial diluted solution, or final dilution for infusion should come into contact with mucosa, immediately and thoroughly wash with water.

Contact of the Docetaxel Injection with plasticized PVC equipment or devices used to prepare solutions for infusion is not recommended. In order to minimize patient exposure to the plasticizer DEHP (di-2-ethylhexyl phthalate), which may be leached from PVC infusion bags or sets, the final Docetaxel Injection dilution for infusion should be stored in bottles (glass, polypropylene) or plastic bags (polypropylene, polyolefin) and administered through polyethylene-lined administration sets.

One-vial Docetaxel Injection

Docetaxel Injection requires NO prior dilution with a diluent and is ready to add to the infusion solution.

Please follow the preparation instructions provided below.

2.9 Preparation and Administration

One-vial Docetaxel Injection

Docetaxel Injection (20 mg/mL) requires NO prior dilution with a diluent and is ready to add to the infusion solution. Use only a 21 gauge needle to withdraw docetaxel from the vial because larger bore needles (e.g., 18 and 19 gauge) may result in stopper coring and rubber particulates.

1. Docetaxel Injection vials should be stored between 15°C and 25°C (59°F and 77°F).
2. Using onlya 21 gauge needle, aseptically withdraw the required amount of Docetaxel injection (20 mg docetaxel/mL) with a calibrated syringe and inject via a single injection (one shot) into a 250 mL infusion bag or bottle of either 0.9% Sodium Chloride solution or 5% Dextrose solution to produce a final concentration of 0.3 mg/mL to 0.74 mg/mL.
  If a dose greater than 200 mg of Docetaxel Injection is required, use a larger volume of the infusion vehicle so that a concentration of 0.74 mg/mL Docetaxel Injection is not exceeded.
3. Thoroughly mix the infusion by gentle manual rotation.
4. As with all parenteral products, Docetaxel Injection should be inspected visually for particulate matter or discoloration prior to administration whenever the solution and container permit. If the Docetaxel Injection dilution for intravenous infusion is not clear or appears to have precipitation, it should be discarded.
5. Docetaxel Injection infusion solution is supersaturated, therefore may crystallize over time. If crystals appear, the solution must no longer be used and shall be discarded.

The docetaxel dilution for infusion should be administered intravenously as a 1-hour infusion under ambient room temperature (below 25°C) and lighting conditions.

2.10 Stability

Docetaxel Injection final dilution for infusion, if stored between 2°C and 25°C (36°F and 77°F) is stable for 6 hours. Docetaxel Injection final dilution for infusion (in either 0.9% Sodium Chloride solution or 5% Dextrose solution) should be used within 6 hours (including the 1 hour intravenous administration).

In addition, physical and chemical in-use stability of the infusion solution prepared as recommended has been demonstrated in non-PVC bags up to 48 hours when stored between 2°C and 8°C (36°F and 46°F).

3 DOSAGE FORMS AND STRENGTHS

One-vial formulation Docetaxel (Injection)

Docetaxel Injection: 160 mg/8 mL solution in multiple-dose vials

Docetaxel Injection: 80 mg/4 mL solution in multiple-dose vials

Docetaxel Injection: 20 mg/mL solution in multiple-dose vials

4 CONTRAINDICATIONS

Docetaxel Injection is contraindicated in patients with:

- neutrophil counts of < 1500 cells/mm^3 [see Warnings and Precautions (5.3)].
- a history of severe hypersensitivity reactions to docetaxel or to other drugs formulated with polysorbate 80. Severe reactions, including anaphylaxis, have occurred [see Warnings and Precautions (5.5)].

5 WARNINGS AND PRECAUTIONS

5.1 Toxic Deaths

Breast Cancer

Docetaxel administered at 100 mg/m^2was associated with deaths considered possibly or probably related to treatment in 2.0% (19/965) of metastatic breast cancer patients, both previously treated and untreated, with normal baseline liver function and in 11.5% (7/61) of patients with various tumor types who had abnormal baseline liver function (AST and/or ALT >1.5 times ULN together with AP >2.5 times ULN). Among patients dosed at 60 mg/m^2, mortality related to treatment occurred in 0.6% (3/481) of patients with normal liver function, and in 3 of 7 patients with abnormal liver function. Approximately half of these deaths occurred during the first cycle. Sepsis accounted for the majority of the deaths.

Non-small Cell Lung Cancer

Docetaxel administered at a dose of 100 mg/m^2in patients with locally advanced or metastatic non-small cell lung cancer who had a history of prior platinum-based chemotherapy was associated with increased treatment-related mortality (14% and 5% in two randomized, controlled studies). There were 2.8% treatment-related deaths among the 176 patients treated at the 75 mg/m^2dose in the randomized trials. Among patients who experienced treatment-related mortality at the 75 mg/m^2dose level, 3 of 5 patients had an ECOG PS of 2 at study entry [see Dosage and Administration (2.2), Clinical Studies (14)].

5.2 Hepatic Impairment

Patients with elevations of bilirubin or abnormalities of transaminase concurrent with alkaline phosphatase are at increased risk for the development of severe neutropenia, febrile neutropenia, infections, severe thrombocytopenia, severe stomatitis, severe skin toxicity, and toxic death.

Avoid Docetaxel Injection in patients with bilirubin > upper limit of normal (ULN), or to patients with AST and/or ALT >1.5 × ULN concomitant with alkaline phosphatase >2.5 × ULN [see Warnings and Precautions (5.1)].

For patients with isolated elevations of transaminase >1.5 × ULN, consider Docetaxel Injection dose modifications [see Dosage and Administration (2.7)].

Measure bilirubin, AST or ALT, and alkaline phosphatase prior to each cycle of Docetaxel Injection therapy.

5.3 Hematologic Effects

Perform frequent peripheral blood cell counts on all patients receiving Docetaxel Injection. Do not retreat patients with subsequent cycles of Docetaxel Injection until neutrophils recover to a level >1500 cells/mm^3 [see Contraindications (4)]. Avoid retreating patients until platelets recover to a level >100,000 cells/mm^3.

A 25% reduction in the dose of Docetaxel Injection is recommended during subsequent cycles following severe neutropenia (<500 cells/mm^3) lasting 7 days or more, febrile neutropenia, or a grade 4 infection in a Docetaxel Injection cycle [see Dosage and Administration (2.7)].

Neutropenia (<2000 neutrophils/mm^3) occurs in virtually all patients given 60 mg/m^2to 100 mg/m^2of Docetaxel Injection and grade 4 neutropenia (<500 cells/mm^3) occurs in 85% of patients given 100 mg/m^2and 75% of patients given 60 mg/m^2. Frequent monitoring of blood counts is, therefore, essential so that dose can be adjusted. Docetaxel Injection should not be administered to patients with neutrophils <1500 cells/mm^3.

Febrile neutropenia occurred in about 12% of patients given 100 mg/m^2but was very uncommon in patients given 60 mg/m^2. Hematologic responses, febrile reactions and infections, and rates of septic death for different regimens are dose related [see Adverse Reactions (6.1), Clinical Studies (14)].

Three breast cancer patients with severe liver impairment (bilirubin >1.7 times ULN) developed fatal gastrointestinal bleeding associated with severe drug-induced thrombocytopenia. In gastric cancer patients treated with docetaxel in combination with cisplatin and fluorouracil (TCF), febrile neutropenia and/or neutropenic infection occurred in 12% of patients receiving G-CSF compared to 28% who did not. Patients receiving TCF should be closely monitored during the first and subsequent cycles for febrile neutropenia and neutropenic infection [see Dosage and Administration (2.7), Adverse Reactions (6)]

5.4 Enterocolitis and Neutropenic Colitis

Enterocolitis and neutropenic colitis (typhlitis) have occurred in patients treated with Docetaxel Injection alone and in combination with other chemotherapeutic agents, despite the coadministration of G-CSF. Caution is recommended for patients with neutropenia, particularly at risk for developing gastrointestinal complications. Enterocolitis and neutropenic enterocolitis may develop at any time, and could lead to death as early as the first day of symptom onset. Monitor patients closely from onset of any symptoms of gastrointestinal toxicity. Inform patients to contact their healthcare provider with new, or worsening symptoms of gastrointestinal toxicity [see Dosage and Administration (2), Warnings and Precautions (5.3), Adverse Reactions (6.2)].

5.5 Hypersensitivity Reactions

Monitor patients closely for hypersensitivity reactions, especially during the first and second infusions. Severe hypersensitivity reactions characterized by generalized rash/erythema, hypotension and/or bronchospasm, or fatal anaphylaxis, have been reported in patients pre-medicated with 3 days of corticosteroids. Severe hypersensitivity reactions require immediate discontinuation of the Docetaxel Injection infusion and aggressive therapy. Do not rechallenge patients with a history of severe hypersensitivity reactions with Docetaxel Injection [see Contraindications (4)].

Patients who have previously experienced a hypersensitivity reaction to paclitaxel may develop a hypersensitivity reaction to docetaxel that may include severe or fatal reactions such as anaphylaxis. Monitor patients with a previous history of hypersensitivity to paclitaxel closely during initiation of docetaxel therapy.

Hypersensitivity reactions may occur within a few minutes following initiation of a Docetaxel Injection infusion. If minor reactions such as flushing or localized skin reactions occur, interruption of therapy is not required. All patients should be premedicated with an oral corticosteroid prior to the initiation of the infusion of Docetaxel Injection [see Dosage and Administration (2.6)] .

5.6 Fluid Retention

Severe fluid retention has been reported following docetaxel therapy. Patients should be premedicated with oral corticosteroids prior to each Docetaxel Injection administration to reduce the incidence and severity of fluid retention [see Dosage and Administration (2.6)]. Patients with pre-existing effusions should be closely monitored from the first dose for the possible exacerbation of the effusions.

When fluid retention occurs, peripheral edema usually starts in the lower extremities and may become generalized with a median weight gain of 2 kg.

Among 92 breast cancer patients premedicated with 3-day corticosteroids, moderate fluid retention occurred in 27.2% and severe fluid retention in 6.5%. The median cumulative dose to onset of moderate or severe fluid retention was 819 mg/m^2. Nine of 92 patients (9.8%) of patients discontinued treatment due to fluid retention: 4 patients discontinued with severe fluid retention; the remaining 5 had mild or moderate fluid retention. The median cumulative dose to treatment discontinuation due to fluid retention was 1021 mg/m^2. Fluid retention was completely, but sometimes slowly, reversible with a median of 16 weeks from the last infusion of docetaxel to resolution (range: 0 to 42+ weeks). Patients developing peripheral edema may be treated with standard measures, e.g., salt restriction, oral diuretic(s).

5.7 Second Primary Malignancies

Second primary malignancies, notably acute myeloid leukemia (AML), myelodysplastic syndrome (MDS), non-Hodgkin’s lymphoma (NHL), and renal cancer, have been reported in patients treated with docetaxel-containing regimens. These adverse reactions may occur several months or years after docetaxel-containing therapy.

Treatment-related AML or MDS has occurred in patients given anthracyclines and/or cyclophosphamide, including use in adjuvant therapy for breast cancer. In the adjuvant breast cancer trial (TAX316) AML occurred in 3 of 744 patients who received docetaxel, doxorubicin and cyclophosphamide (TAC) and in 1 of 736 patients who received fluorouracil, doxorubicin, and cyclophosphamide In TAC-treated patients, the risk of delayed myelodysplasia or myeloid leukemia requires hematological follow-up. Monitor patients for second primary malignancies Treatment-related AML or MDS has occurred in patients given anthracyclines and/or cyclophosphamide, including use in adjuvant therapy for breast cancer. In the adjuvant breast cancer trial (TAX316) AML occurred in 3 of 744 patients who received docetaxel, doxorubicin and cyclophosphamide (TAC) and in 1 of 736 patients who received fluorouracil, doxorubicin, and cyclophosphamide [see Clinical Studies (14.2)]. In TAC-treated patients, the risk of delayed myelodysplasia or myeloid leukemia requires hematological follow-up. Monitor patients for second primary malignancies [see Adverse Reactions (6.1)].

5.8 Cutaneous Reactions

Localized erythema of the extremities with edema followed by desquamation has been observed. In case of severe skin toxicity, an adjustment in dosage is recommended The discontinuation rate due to skin toxicity was 1.6% (15/965) for metastatic breast cancer patients. Among 92 breast cancer patients premedicated with 3-day corticosteroids, there were no cases of severe skin toxicity reported and no patient discontinued docetaxel due to skin toxicity. Localized erythema of the extremities with edema followed by desquamation has been observed. In case of severe skin toxicity, an adjustment in dosage is recommended [see Dosage and Administration (2.7)]. The discontinuation rate due to skin toxicity was 1.6% (15/965) for metastatic breast cancer patients. Among 92 breast cancer patients premedicated with 3-day corticosteroids, there were no cases of severe skin toxicity reported and no patient discontinued docetaxel due to skin toxicity.

Severe cutaneous adverse reactions (SCARs) such as Stevens-Johnson syndrome (SJS), toxic epidermal necrolysis (TEN), and acute generalized exanthematous pustulosis (AGEP) have been reported in association with docetaxel treatment. Patients should be informed about the signs and symptoms of serious skin manifestations and monitored closely. Permanent treatment discontinuation should be considered in patients who experience SCARs.

5.9 Neurologic Reactions

Severe neurosensory symptoms (e.g. paresthesia, dysesthesia, pain) were observed in 5.5% (53/965) of metastatic breast cancer patients, and resulted in treatment discontinuation in 6.1%. When these symptoms occur, dosage must be adjusted. If symptoms persist, treatment should be discontinued [see Dosage and Administration (2.7)]. Patients who experienced neurotoxicity in clinical trials and for whom follow-up information on the complete resolution of the event was available had spontaneous reversal of symptoms with a median of 9 weeks from onset (range: 0 to 106 weeks). Severe peripheral motor neuropathy mainly manifested as distal extremity weakness occurred in 4.4% (42/965).

5.10 Eye Disorders

Cystoid macular edema (CME) has been reported in patients treated with Docetaxel Injection. Patients with impaired vision should undergo a prompt and comprehensive ophthalmologic examination. If CME is diagnosed, Docetaxel Injection treatment should be discontinued and appropriate treatment initiated. Alternative non-taxane cancer treatment should be considered.

5.11 Asthenia

Severe asthenia has been reported in 14.9% (144/965) of metastatic breast cancer patients but has led to treatment discontinuation in only 1.8%. Symptoms of fatigue and weakness may last a few days up to several weeks and may be associated with deterioration of performance status in patients with progressive disease.

5.12 Embryo-Fetal Toxicity

Based on findings from animal reproduction studies and its mechanism of action, docetaxel can cause fetal harm when administered to a pregnant woman [see Clinical Pharmacology (12.1)]. Available data from case reports in the literature and pharmacovigilance with docetaxel use in pregnant women are not sufficient to inform the drug-associated risk of major birth defects, miscarriage or adverse maternal or fetal outcomes. In animal reproduction studies, administration of docetaxel to pregnant rats and rabbits during the period of organogenesis caused embryo-fetal toxicities, including intrauterine mortality, at doses as low as 0.02 and 0.003 times the recommended human dose based on body surface area, respectively.

Advise pregnant women and females of reproductive potential of the potential risk to a fetus. Verify pregnancy status in females of reproductive potential prior to initiating docetaxel. Advise females of reproductive potential to use effective contraception during treatment and for 2 months after the last dose of docetaxel. Advise male patients with female partners of reproductive potential to use effective contraception during treatment and for 4 months after the last dose of docetaxel [see Use in Specific Populations (8.1, 8.3)].

5.13 Alcohol Content

Cases of intoxication have been reported with some formulations of docetaxel due to the alcohol content. The alcohol content in a dose of Docetaxel Injection may affect the central nervous system and should be taken into account for patients in whom alcohol intake should be avoided or minimized. Consideration should be given to the alcohol content in Docetaxel Injection on the ability to drive or use machines immediately after the infusion.

Each administration of Docetaxel Injection at 100 mg/m^2delivers 1.975 g/m^2of ethanol. For a patient with a BSA of 2.0 m^2, this would deliver 3.95 grams of ethanol [see Description (11)] . Other docetaxel products may have a different amount of alcohol.

5.14 Tumor Lysis Syndrome

Tumor lysis syndrome has been reported with docetaxel [see Adverse Reactions (6.2)] . Patients at risk of tumor lysis syndrome (e.g., with renal impairment, hyperuricemia, bulky tumor) should be closely monitored prior to initiating Docetaxel Injection and periodically during treatment. Correction of dehydration and treatment of high uric acid levels are recommended prior to initiation of treatment.

6 ADVERSE REACTIONS

The most serious adverse reactions from docetaxel are:

- Toxic Deaths [see Boxed Warning, Warnings and Precautions (5.1)]
- Hepatic Impairment [see Boxed Warning, Warnings and Precautions (5.2)]
- Hematologic Effects [see Boxed Warning, Warnings and Precautions (5.3)]
- Enterocolitis and Neutropenic Colitis [see Warnings and Precautions (5.4)]
- Hypersensitivity Reactions [see Boxed Warning, Warnings and Precautions (5.5)]
- Fluid Retention [see Boxed Warning, Warnings and Precautions (5.6)]
- Second Primary Malignancies [see Warnings and Precautions (5.7)]
- Cutaneous Reactions [see Warnings and Precautions (5.8)]
- Neurologic Reactions [see Warnings and Precautions (5.9)]
- Eye Disorders [see Warnings and Precautions (5.10)]
- Asthenia [see Warnings and Precautions (5.11)]
- Alcohol Content [see Warnings and Precautions (5.13)]

The most common adverse reactions across all docetaxel indications are infections, neutropenia, anemia, febrile neutropenia, hypersensitivity, thrombocytopenia, neuropathy, dysgeusia, dyspnea, constipation, anorexia, nail disorders, fluid retention, asthenia, pain, nausea, diarrhea, vomiting, mucositis, alopecia, skin reactions, and myalgia. Incidence varies depending on the indication.

Adverse reactions are described according to indication. Because clinical trials are conducted under widely varying conditions, adverse reaction rates observed in the clinical trials of a drug cannot be directly compared to rates in the clinical trials of another drug and may not reflect the rates observed in practice.

Responding patients may not experience an improvement in performance status on therapy and may experience worsening. The relationship between changes in performance status, response to therapy, and treatment-related side effects has not been established.

6.1 Clinical Trials Experience

Breast Cancer

Monotherapy with docetaxel for locally advanced or metastatic breast cancer after failure of prior chemotherapy

Docetaxel 100 mg/m^2: Adverse drug reactions occurring in at least 5% of patients are compared for three populations who received docetaxel administered at 100 mg/m^2as a 1-hour infusion every 3 weeks: 2045 patients with various tumor types and normal baseline liver function tests; the subset of 965 patients with locally advanced or metastatic breast cancer, both previously treated and untreated with chemotherapy, who had normal baseline liver function tests; and an additional 61 patients with various tumor types who had abnormal liver function tests at baseline. These reactions were described using COSTART terms and were considered possibly or probably related to docetaxel. At least 95% of these patients did not receive hematopoietic support. The safety profile is generally similar in patients receiving docetaxel for the treatment of breast cancer and in patients with other tumor types. (See Table 3.)

Table 3 : Summary of Adverse Reactions in Patients Receiving Docetaxel at 100 mg/m^2
Adverse Reaction | All Tumor Types Normal LFTs [Normal Baseline LFTs: Transaminases ≤1.5 times ULN or alkaline phosphatase ≤2.5 times ULN or isolated elevations of transaminases or alkaline phosphatase up to 5 times ULN] n=2045 % | All Tumor Types Elevated LFTs [Elevated Baseline LFTs: AST and/or ALT >1.5 times ULN concurrent with alkaline phosphatase >2.5 times ULN] n=61 % | Breast Cancer Normal LFTs n=965 %
Hematologic
Neutropenia
<2000 cells/mm^3 | 96 | 96 | 99
<500 cells/mm^3 Leukopenia | 75 | 88 | 86
<4000 cells/mm^3 | 96 | 98 | 99
<1000 cells/mm^3 Thrombocytopenia | 32 | 47 | 44
<100,000 cells/mm^3 | 8 | 25 | 9
Anemia <11 g/dL | 90 | 92 | 94
<8 g/dL | 9 | 31 | 8
Febrile Neutropenia [Febrile Neutropenia: ANC grade 4 with fever >38°C with intravenous antibiotics and/or hospitalization] | 11 | 26 | 12
Septic Death | 2 | 5 | 1
Non-Septic Death | 1 | 7 | 1
Infections
Any | 22 | 33 | 22
Severe | 6 | 16 | 6
Fever in Absence of Infection
Any | 31 | 41 | 35
Severe | 2 | 8 | 2
Hypersensitivity Reactions
Regardless of Premedication
Any | 21 | 20 | 18
Severe | 4 | 10 | 3
With 3-day Premedication | n=92 | n=3 | n=92
Any | 15 | 33 | 15
Severe | 2 | 0 | 2
Fluid Retention
Regardless of Premedication
Any | 47 | 39 | 60
Severe | 7 | 8 | 9
With 3-day Premedication | n=92 | n=3 | n=92
Any | 64 | 67 | 64
Severe | 7 | 33 | 7
Neurosensory
Any | 49 | 34 | 58
Severe | 4 | 0 | 6
Cutaneous
Any | 48 | 54 | 47
Severe | 5 | 10 | 5
Nail Changes
Any | 31 | 23 | 41
Severe | 3 | 5 | 4
Gastrointestinal
Nausea | 39 | 38 | 42
Vomiting | 22 | 23 | 23
Diarrhea | 39 | 33 | 43
Severe | 5 | 5 | 6
Stomatitis
Any | 42 | 49 | 52
Severe | 6 | 13 | 7
Alopecia | 76 | 62 | 74
Asthenia
Any | 62 | 53 | 66
Severe | 13 | 25 | 15
Myalgia
Any | 19 | 16 | 21
Severe | 2 | 2 | 2
Arthralgia | 9 | 7 | 8
Infusion Site Reactions | 4 | 3 | 4

Hematologic reactions

Reversible marrow suppression was the major dose-limiting toxicity of docetaxel [see Warnings and Precautions (5.3)]. The median time to nadir was 7 days, while the median duration of severe neutropenia (<500 cells/mm^3) was 7 days. Among 2045 patients with solid tumors and normal baseline LFTs, severe neutropenia occurred in 75.4% and lasted for more than 7 days in 2.9% of cycles.

Febrile neutropenia (<500 cells/mm^3with fever >38°C with intravenous antibiotics and/or hospitalization) occurred in 11% of patients with solid tumors, in 12.3% of patients with metastatic breast cancer, and in 9.8% of 92 breast cancer patients premedicated with 3-day corticosteroids.

Severe infectious episodes occurred in 6.1% of patients with solid tumors, in 6.4% of patients with metastatic breast cancer, and in 5.4% of 92 breast cancer patients premedicated with 3-day corticosteroids. Thrombocytopenia (<100,000 cells/mm3) associated with fatal gastrointestinal hemorrhage has been reported.

Hypersensitivity reactions

Severe hypersensitivity reactions have been reported [see Boxed Warning, Warnings and Precautions (5.5)] . Minor events, including flushing, rash with or without pruritus, chest tightness, back pain, dyspnea, drug fever, or chills, have been reported and resolved after discontinuing the infusion and instituting appropriate therapy.

Fluid retention

Fluid retention can occur with the use of docetaxel [see Boxed Warning, Dosage and Administration (2.6), Warnings and Precautions (5.6)].

Cutaneous reactions

Severe skin toxicity is discussed elsewhere in the label [see Warnings and Precautions (5.8)]. Reversible cutaneous reactions characterized by a rash including localized eruptions, mainly on the feet and/or hands, but also on the arms, face, or thorax, usually associated with pruritus, have been observed. Eruptions generally occurred within 1 week after docetaxel infusion, recovered before the next infusion, and were not disabling.

Severe nail disorders were characterized by hypo or hyperpigmentation, and occasionally by onycholysis (in 0.8% of patients with solid tumors) and pain.

Neurologic reactions

Neurologic reactions are discussed elsewhere in the label [see Warnings and Precautions (5.9)].

Gastrointestinal reactions

Nausea, vomiting, and diarrhea were generally mild to moderate. Severe reactions occurred in 3%-5% of patients with solid tumors and to a similar extent among metastatic breast cancer patients. The incidence of severe reactions was 1% or less for the 92 breast cancer patients premedicated with 3-day corticosteroids.

Severe stomatitis occurred in 5.5% of patients with solid tumors, in 7.4% of patients with metastatic breast cancer, and in 1.1% of the 92 breast cancer patients premedicated with 3-day corticosteroids.

Cardiovascular reactions

Hypotension occurred in 2.8% of patients with solid tumors; 1.2% required treatment. Clinically meaningful events such as heart failure, sinus tachycardia, atrial flutter, dysrhythmia, unstable angina, pulmonary edema, and hypertension have occurred. Seven of 86 (8.1%) of metastatic breast cancer patients receiving docetaxel 100 mg/m^2in a randomized trial and who had serial left ventricular ejection fractions assessed developed deterioration of LVEF by ≥10% associated with a drop below the institutional lower limit of normal.

Infusion site reactions

Infusion site reactions were generally mild and consisted of hyperpigmentation, inflammation, redness or dryness of the skin, phlebitis, extravasation, or swelling of the vein.

Hepatic reactions

In patients with normal LFTs at baseline, bilirubin values greater than the ULN occurred in 8.9% of patients. Increases in AST or ALT >1.5 times the ULN, or alkaline phosphatase >2.5 times ULN, were observed in 18.9% and 7.3% of patients, respectively. While on docetaxel, increases in AST and/or ALT >1.5 times ULN concomitant with alkaline phosphatase >2.5 times ULN occurred in 4.3% of patients with normal LFTs at baseline. Whether these changes were related to the drug or underlying disease has not been established.

Hematologic and other toxicity: Relation to dose and baseline liver chemistry abnormalities

Hematologic and other toxicity is increased at higher doses and in patients with elevated baseline liver function tests (LFTs). In the following tables, adverse drug reactions are compared for three populations: 730 patients with normal LFTs given docetaxel at 100 mg/m^2in the randomized and single arm studies of metastatic breast cancer after failure of previous chemotherapy; 18 patients in these studies who had abnormal baseline LFTs (defined as AST and/or ALT >1.5 times ULN concurrent with alkaline phosphatase >2.5 times ULN); and 174 patients in Japanese studies given docetaxel at 60 mg/m^2who had normal LFTs (see Tables 4and 5).

Table 4: Hematologic Adverse Reactions in Breast Cancer Patients Previously Treated with Chemotherapy Treated at Docetaxel 100 mg/m^2with Normal or Elevated Liver Function Tests or 60 mg/m^2with Normal Liver Function Tests
 | Docetaxel 100 mg/m^2 |  | Docetaxel 60 mg/m^2
 | Normal LFTs [Normal Baseline LFTs: Transaminases ≤1.5 times ULN or alkaline phosphatase ≤2.5 times ULN or isolated elevations of transaminases or alkaline phosphatase up to 5 times ULN] | Elevated LFTs [Elevated Baseline LFTs: AST and/or ALT >1.5 times ULN concurrent with alkaline phosphatase >2.5 times ULN] | Normal LFTs
Adverse Reaction | n=730 | n=18 | n=174
 | % | % | %
Neutropenia
Any <2000 cells/mm^3 | 98 | 100 | 95
Grade 4 <500 cells/mm^3 | 84 | 94 | 75
Thrombocytopenia
Any <100,000 cells/mm^3 | 11 | 44 | 14
Grade 4 <20,000 cells/mm^3 | 1 | 17 | 1
Anemia <11 g/dL | 95 | 94 | 65
Infection [Incidence of infection requiring hospitalization and/or intravenous antibiotics was 8.5% (n=62) among the 730 patients with normal LFTs at baseline; 7 patients had concurrent grade 3 neutropenia, and 46 patients had grade 4 neutropenia.]
Any | 23 | 39 | 1
Grade 3 and 4 | 7 | 33 | 0
Febrile Neutropenia [Febrile Neutropenia: For 100 mg/m 2, ANC grade 4 and fever >38°C with intravenous antibiotics and/or hospitalization; for 60 mg/m 2, ANC grade 3/4 and fever >38.1°C]
By Patient | 12 | 33 | 0
By Course | 2 | 9 | 0
Septic Death | 2 | 6 | 1
Non-Septic Death | 1 | 11 | 0

Table 5: Non-hematologic Adverse Reactions in Breast Cancer Patients Previously Treated with Chemotherapy Treated at Docetaxel 100 mg/m^2with Normal or Elevated Liver Function Tests or 60 mg/m^2with Normal Liver Function Tests
 | Docetaxel 100 mg/m^2 |  | Docetaxel 60 mg/m^2
 | Normal LFTs [Normal Baseline LFTs: Transaminases ≤1.5 times ULN or alkaline phosphatase ≤2.5 times ULN or isolated elevations of transaminases or alkaline phosphatase up to 5 times ULN] | Elevated LFTs [Elevated Baseline Liver Function: AST and/or ALT >1.5 times ULN concurrent with alkaline phosphatase >2.5 times ULN] | Normal LFTs
Adverse Reaction | n=730 | n=18 | n=174
 | % | % | %
Acute Hypersensitivity Reaction Regardless of Premedication
Any | 13 | 6 | 1
Severe | 1 | 0 | 0
Fluid Retention [Fluid Retention includes (by COSTART): edema (peripheral, localized, generalized, lymphedema, pulmonary edema, and edema otherwise not specified) and effusion (pleural, pericardial, and ascites); no premedication given with the 60 mg/m 2 dose] Regardless of Premedication
Any | 56 | 61 | 13
Severe | 8 | 17 | 0
Neurosensory
Any | 57 | 50 | 20
Severe | 6 | 0 | 0
Myalgia | 23 | 33 | 3
Cutaneous
Any | 45 | 61 | 31
Severe | 5 | 17 | 0
Asthenia
Any | 65 | 44 | 66
Severe | 17 | 22 | 0
Diarrhea
Any | 42 | 28 | NA
Severe | 6 | 11
Stomatitis
Any | 53 | 67 | 19
Severe | 8 | 39 | 1
NA = not available

In the three-arm monotherapy trial, TAX313, which compared docetaxel 60 mg/m^2, 75 mg/m^2and 100 mg/m^2in advanced breast cancer, grade 3/4 or severe adverse reactions occurred in 49.0% of patients treated with docetaxel 60 mg/m^2compared to 55.3% and 65.9% treated with 75 mg/m^2and 100 mg/m^2respectively. Discontinuation due to adverse reactions was reported in 5.3% of patients treated with 60 mg/m^2versus 6.9% and 16.5% for patients treated at 75 and 100 mg/m^2, respectively. Deaths within 30 days of last treatment occurred in 4.0% of patients treated with 60 mg/m^2compared to 5.3% and 1.6% for patients treated at 75 mg/m^2and 100 mg/m^2, respectively.

The following adverse reactions were associated with increasing docetaxel doses: fluid retention (26%, 38%, and 46% at 60 mg/m^2, 75 mg/m^2, and 100 mg/m^2respectively), thrombocytopenia (7%, 11% and 12%, respectively), neutropenia (92%, 94%, and 97% respectively), febrile neutropenia (5%, 7%, and 14%, respectively), treatment-related grade 3/4 infection (2%, 3%, and 7%, respectively) and anemia (87%, 94%, and 97%, respectively).

Combination therapy with docetaxel in the adjuvant treatment of breast cancer

The following table presents treatment emergent adverse reactions observed in 744 patients, who were treated with docetaxel 75 mg/m^2every 3 weeks in combination with doxorubicin and cyclophosphamide (see Table 6).

Table 6: Clinically Important Treatment-Emergent Adverse Reactions Regardless of Causal Relationship in Patients Receiving Docetaxel in Combination with Doxorubicin and Cyclophosphamide (TAX316).
 | Docetaxel 75 mg/m^2+ Doxorubicin 50 mg/m^2+ Cyclophosphamide 500 mg/m^2(TAC) n=744 % |  | Fluorouracil 500 mg/m^2+ Doxorubicin 50 mg/m^2+ Cyclophosphamide 500 mg/m^2(FAC) n=736 %
Adverse Reaction | Any | Grade 3/4 | Any | Grade 3/4
Anemia | 92 | 4 | 72 | 2
Neutropenia | 71 | 66 | 82 | 49
Fever in absence of infection | 47 | 1 | 17 | 0
Infection | 39 | 4 | 36 | 2
Thrombocytopenia | 39 | 2 | 28 | 1
Febrile neutropenia | 25 | N/A | 3 | N/A
Neutropenic infection | 12 | N/A | 6 | N/A
Hypersensitivity reactions | 13 | 1 | 4 | 0
Lymphedema | 4 | 0 | 1 | 0
Fluid Retention [COSTART term and grading system for events related to treatment.] | 35 | 1 | 15 | 0
Peripheral edema | 27 | 0 | 7 | 0
Weight gain | 13 | 0 | 9 | 0
Neuropathy sensory | 26 | 0 | 10 | 0
Neuro-cortical | 5 | 1 | 6 | 1
Neuropathy motor | 4 | 0 | 2 | 0
Neuro-cerebellar | 2 | 0 | 2 | 0
Syncope | 2 | 1 | 1 | 0
Alopecia | 98 | N/A | 97 | N/A
Skin toxicity | 27 | 1 | 18 | 0
Nail disorders | 19 | 0 | 14 | 0
Nausea | 81 | 5 | 88 | 10
Stomatitis | 69 | 7 | 53 | 2
Vomiting | 45 | 4 | 59 | 7
Diarrhea | 35 | 4 | 28 | 2
Constipation | 34 | 1 | 32 | 1
Taste perversion | 28 | 1 | 15 | 0
Anorexia | 22 | 2 | 18 | 1
Abdominal Pain | 11 | 1 | 5 | 0
Amenorrhea | 62 | N/A | 52 | N/A
Cough | 14 | 0 | 10 | 0
Cardiac dysrhythmias | 8 | 0 | 6 | 0
Vasodilatation | 27 | 1 | 21 | 1
Hypotension | 2 | 0 | 1 | 0
Phlebitis | 1 | 0 | 1 | 0
Asthenia | 81 | 11 | 71 | 6
Myalgia | 27 | 1 | 10 | 0
Arthralgia | 19 | 1 | 9 | 0
Lacrimation disorder | 11 | 0 | 7 | 0
Conjunctivitis | 5 | 0 | 7 | 0

Of the 744 patients treated with TAC, 36.3% experienced severe treatment-emergent adverse reactions compared to 26.6% of the 736 patients treated with FAC. Dose reductions due to hematologic toxicity occurred in 1% of cycles in the TAC arm versus 0.1% of cycles in the FAC arm. Six percent of patients treated with TAC discontinued treatment due to adverse reactions, compared to 1.1% treated with FAC; fever in the absence of infection and allergy being the most common reasons for withdrawal among TAC-treated patients. Two patients died in each arm within 30 days of their last study treatment; 1 death per arm was attributed to study drugs.

Fever and infection

During the treatment period, fever in the absence of infection was seen in 46.5% of TAC-treated patients and in 17.1% of FAC-treated patients. Grade 3/4 fever in the absence of infection was seen in 1.3% and 0% of TAC and FAC-treated patients respectively. Infection was seen in 39.4% of TAC-treated patients compared to 36.3% of FAC-treated patients. Grade 3/4 infection was seen in 3.9% and 2.2% of TAC-treated and FAC-treated patients respectively. There were no septic deaths in either treatment arm during the treatment period.

Gastrointestinal reactions

In addition to gastrointestinal reactions reflected in the table above, 7 patients in the TAC arm were reported to have colitis/enteritis/large intestine perforation versus one patient in the FAC arm. Five of the 7 TAC-treated patients required treatment discontinuation; no deaths due to these events occurred during the treatment period.

Cardiovascular reactions

More cardiovascular reactions were reported in the TAC arm versus the FAC arm during the treatment period: arrhythmias, all grades (6.2% vs 4.9%), and hypotension, all grades (1.9% vs 0.8%). Twenty-six (26) patients (3.5%) in the TAC arm and 17 patients (2.3%) in the FAC arm developed CHF during the study period. All except one patient in each arm were diagnosed with CHF during the follow-up period. Two (2) patients in TAC arm and 4 patients in FAC arm died due to CHF. The risk of CHF was higher in the TAC arm in the first year, and then was similar in both treatment arms.

Adverse reactions during the follow-up period (median follow-up time of 8 years)

In study TAX316, the most common adverse reactions that started during the treatment period and persisted into the follow-up period in TAC and FAC patients are described below (median follow-up time of 8 years).

Nervous system disorders

In study TAX316, peripheral sensory neuropathy started during the treatment period and persisted into the follow-up period in 84 patients (11.3%) in TAC arm and 15 patients (2%) in FAC arm. At the end of the follow-up period (median follow-up time of 8 years), peripheral sensory neuropathy was observed to be ongoing in 10 patients (1.3%) in TAC arm, and in 2 patients (0.3%) in FAC arm.

Skin and subcutaneous tissue disorders

In study TAX316, alopecia persisting into the follow-up period after the end of chemotherapy was reported in 687 of 744 TAC patients (92.3%) and 645 of 736 FAC patients (87.6%). At the end of the follow-up period (actual median follow-up time of 8 years), alopecia was observed to be ongoing in 29 TAC patients (3.9%) and 16 FAC patients (2.2%).

Reproductive system and breast disorders

In study TAX316, amenorrhea that started during the treatment period and persisted into the follow-up period after the end of chemotherapy was reported in 202 of 744 TAC patients (27.2%) and 125 of 736 FAC patients (17.0%). Amenorrhea was observed to be ongoing at the end of the follow-up period (median follow-up time of 8 years) in 121 of 744 TAC patients (16.3%) and 86 FAC patients (11.7%).

General disorders and administration site conditions

In study TAX316, peripheral edema that started during the treatment period and persisted into the follow-up period after the end of chemotherapy was observed in 119 of 744 TAC patients (16.0%) and 23 of 736 FAC patients (3.1%). At the end of the follow-up period (actual median follow-up time of 8 years), peripheral edema was ongoing in 19 TAC patients (2.6%) and 4 FAC patients (0.5%).

In study TAX316, lymphedema that started during the treatment period and persisted into the follow-up period after the end of chemotherapy was reported in 11 of 744 TAC patients (1.5%) and 1 of 736 FAC patients (0.1%). At the end of the follow-up period (actual median follow-up time of 8 years), lymphedema was observed to be ongoing in 6 TAC patients (0.8%) and 1 FAC patient (0.1%).

In study TAX316, asthenia that started during the treatment period and persisted into the follow-up period after the end of chemotherapy was reported in 236 of 744 TAC patients (31.7%) and 180 of 736 FAC patients (24.5%). At the end of the follow-up period (actual median follow-up time of 8 years), asthenia was observed to be ongoing in 29 TAC patients (3.9%) and 16 FAC patients (2.2%).

Acute myeloid leukemia (AML)/ Myelodysplastic syndrome (MDS)

AML occurred in the adjuvant breast cancer trial (TAX316). The cumulative risk of developing treatment-related AML at median follow-up time of 8 years in TAX316 was 0.4% for TAC-treated patients and 0.1% for FAC-treated patients. One TAC patient (0.1%) and 1 FAC patient (0.1%) died due to AML during the follow-up period (median follow-up time of 8 years). Myelodysplastic syndrome occurred in 2 of 744 (0.3%) patients who received TAC and in 1 of 736 (0.1%) patients who received FAC. AML occurs at a higher frequency when these agents are given in combination with radiation therapy.

Lung Cancer

Monotherapy with docetaxel for unresectable, locally advanced or metastatic NSCLC previously treated with platinum-based chemotherapy

Docetaxel 75 mg/m^2: Treatment-emergent adverse drug reactions are shown in Table 7. Included in this table are safety data for a total of 176 patients with non-small cell lung carcinoma and a history of prior treatment with platinum-based chemotherapy who were treated in two randomized, controlled trials. These reactions were described using NCI Common Toxicity Criteria regardless of relationship to study treatment, except for the hematologic toxicities or where otherwise noted.

Table 7: Treatment-Emergent Adverse Reactions Regardless of Relationship to Treatment in Patients Receiving Docetaxel as Monotherapy for Non-small Cell Lung Cancer Previously Treated with Platinum-Based Chemotherapy [Normal Baseline LFTs: Transaminases ≤1.5 times ULN or alkaline phosphatase ≤2.5 times ULN or isolated elevations of transaminases or alkaline phosphatase up to 5 times ULN]
Adverse Reaction | Docetaxel 75 mg/m^2 n=176 % | Best Supportive Care n=49 % | Vinorelbine/Ifosfamide n=119 %
Neutropenia
Any | 84 | 14 | 83
Grade 3/4 | 65 | 12 | 57
Leukopenia
Any | 84 | 6 | 89
Grade 3/4 | 49 | 0 | 43
Thrombocytopenia
Any | 8 | 0 | 8
Grade 3/4 | 3 | 0 | 2
Anemia
Any | 91 | 55 | 91
Grade 3/4 | 9 | 12 | 14
Febrile Neutropenia [Febrile Neutropenia: ANC grade 4 with fever >38°C with intravenous antibiotics and/or hospitalization] | 6 | NA [Not Applicable;] | 1
Infection
Any | 34 | 29 | 30
Grade 3/4 | 10 | 6 | 9
Treatment Related Mortality | 3 | NA | 3
Hypersensitivity Reactions
Any | 6 | 0 | 1
Grade 3/4 | 3 | 0 | 0
Fluid Retention
Any | 34 | ND [Not Done] | 23
Severe | 3 |  | 3
Neurosensory
Any | 23 | 14 | 29
Grade 3/4 | 2 | 6 | 5
Neuromotor
Any | 16 | 8 | 10
Grade 3/4 | 5 | 6 | 3
Skin
Any | 20 | 6 | 17
Grade 3/4 | 1 | 2 | 1
Gastrointestinal
Nausea
Any | 34 | 31 | 31
Grade 3/4 | 5 | 4 | 8
Vomiting
Any | 22 | 27 | 22
Grade 3/4 | 3 | 2 | 6
Diarrhea
Any | 23 | 6 | 12
Grade 3/4 | 3 | 0 | 4
Alopecia | 56 | 35 | 50
Asthenia
Any | 53 | 57 | 54
Severe [COSTART term and grading system] | 18 | 39 | 23
Stomatitis
Any | 26 | 6 | 8
Grade 3/4 | 2 | 0 | 1
Pulmonary
Any | 41 | 49 | 45
Grade 3/4 | 21 | 29 | 19
Nail Disorder
Any | 11 | 0 | 2
Severe | 1 | 0 | 0
Myalgia
Any | 6 | 0 | 3
Severe | 0 | 0 | 0
Arthralgia
Any | 3 | 2 | 2
Severe | 0 | 0 | 1
Taste Perversion
Any | 6 | 0 | 0
Severe | 1 | 0 | 0

Combination therapy with docetaxel in chemotherapy-naive advanced unresectable or metastatic NSCLC

Table 8presents safety data from two arms of an open label, randomized controlled trial (TAX326) that enrolled patients with unresectable stage IIIB or IV non-small cell lung cancer and no history of prior chemotherapy. Adverse reactions were described using the NCI Common Toxicity Criteria except where otherwise noted.

Table 8: Adverse Reactions Regardless of Relationship to Treatment in Chemotherapy- Naive Advanced Non-small Cell Lung Cancer Patients Receiving Docetaxel in Combination with Cisplatin
Adverse Reaction | Docetaxel 75 mg/m^2+ Cisplatin 75 mg/m^2 n=406 % | Vinorelbine 25 mg/m^2+ Cisplatin 100 mg/m^2 n=396 %
Neutropenia
Any | 91 | 90
Grade 3/4 | 74 | 78
Febrile Neutropenia | 5 | 5
Thrombocytopenia
Any | 15 | 15
Grade 3/4 | 3 | 4
Anemia
Any | 89 | 94
Grade 3/4 | 7 | 25
Infection
Any | 35 | 37
Grade 3/4 | 8 | 8
Fever in absence of infection
Any | 33 | 29
Grade 3/4 | < 1 | 1
Hypersensitivity Reaction [Replaces NCI term "Allergy"]
Any | 12 | 4
Grade 3/4 | 3 | < 1
Fluid Retention [COSTART term and grading system]
Any | 54 | 42
All severe or life-threatening events | 2 | 2
Pleural effusion
Any | 23 | 22
All severe or life-threatening events | 2 | 2
Peripheral edema
Any | 34 | 18
All severe or life-threatening events | <1 | <1
Weight gain
Any | 15 | 9
All severe or life-threatening events | <1 | <1
Neurosensory
Any | 47 | 42
Grade 3/4 | 4 | 4
Neuromotor
Any | 19 | 17
Grade 3/4 | 3 | 6
Skin
Any | 16 | 14
Grade 3/4 | <1 | 1
Nausea
Any | 72 | 76
Grade 3/4 | 10 | 17
Vomiting
Any | 55 | 61
Grade 3/4 | 8 | 16
Diarrhea
Any | 47 | 25
Grade 3/4 | 7 | 3
Anorexia
Any | 42 | 40
All severe or life-threatening events | 5 | 5
Stomatitis
Any | 24 | 21
Grade 3/4 | 2 | 1
Alopecia
Any | 75 | 42
Grade 3 | <1 | 0
Asthenia
Any | 74 | 75
All severe or life-threatening events | 12 | 14
Nail Disorder
Any | 14 | <1
All severe events | <1 | 0
Myalgia
Any | 18 | 12
All severe events | <1 | <1

Deaths within 30 days of last study treatment occurred in 31 patients (7.6%) in the docetaxel+cisplatin arm and 37 patients (9.3%) in the vinorelbine+cisplatin arm. Deaths within 30 days of last study treatment attributed to study drug occurred in 9 patients (2.2%) in the docetaxel+cisplatin arm and 8 patients (2.0%) in the vinorelbine+cisplatin arm.

The second comparison in the study, vinorelbine+cisplatin versus docetaxel+carboplatin (which did not demonstrate a superior survival associated with docetaxel [see Clinical Studies (14.3)]) demonstrated a higher incidence of thrombocytopenia, diarrhea, fluid retention, hypersensitivity reactions, skin toxicity, alopecia and nail changes on the docetaxel+carboplatin arm, while a higher incidence of anemia, neurosensory toxicity, nausea, vomiting, anorexia and asthenia was observed on the vinorelbine+cisplatin arm.

Prostate Cancer

Combination therapy with docetaxel in patients with prostate cancer

The following data are based on the experience of 332 patients, who were treated with docetaxel 75 mg/m^2every 3 weeks in combination with prednisone 5 mg orally twice daily (see Table 9).

Table 9: Clinically Important Treatment-Emergent Adverse Reactions (Regardless of Relationship) in Patients with Prostate Cancer Who Received Docetaxel in Combination with Prednisone (TAX327)
 | Docetaxel 75 mg/m^2every 3 weeks + prednisone 5 mg twice daily n=332 % |  | Mitoxantrone 12 mg/m^2every 3 weeks + prednisone 5 mg twice daily n=335 %
Adverse Reaction | Any | Grade 3/4 | Any | Grade 3/4
Anemia | 67 | 5 | 58 | 2
Neutropenia | 41 | 32 | 48 | 22
Thrombocytopenia | 3 | 1 | 8 | 1
Febrile neutropenia | 3 | N/A | 2 | N/A
Infection | 32 | 6 | 20 | 4
Epistaxis | 6 | 0 | 2 | 0
Allergic Reactions | 8 | 1 | 1 | 0
Fluid Retention [Related to treatment] | 24 | 1 | 5 | 0
Weight Gain | 8 | 0 | 3 | 0
Peripheral Edema | 18 | 0 | 2 | 0
Neuropathy Sensory | 30 | 2 | 7 | 0
Neuropathy Motor | 7 | 2 | 3 | 1
Rash/Desquamation | 6 | 0 | 3 | 1
Alopecia | 65 | N/A | 13 | N/A
Nail Changes | 30 | 0 | 8 | 0
Nausea | 41 | 3 | 36 | 2
Diarrhea | 32 | 2 | 10 | 1
Stomatitis/Pharyngitis | 20 | 1 | 8 | 0
Taste Disturbance | 18 | 0 | 7 | 0
Vomiting | 17 | 2 | 14 | 2
Anorexia | 17 | 1 | 14 | 0
Cough | 12 | 0 | 8 | 0
Dyspnea | 15 | 3 | 9 | 1
Cardiac left ventricular function | 10 | 0 | 22 | 1
Fatigue | 53 | 5 | 35 | 5
Myalgia | 15 | 0 | 13 | 1
Tearing | 10 | 1 | 2 | 0
Arthralgia | 8 | 1 | 5 | 1

Gastric Cancer

Combination therapy with docetaxel in gastric adenocarcinoma

Data in the following table are based on the experience of 221 patients with advanced gastric adenocarcinoma and no history of prior chemotherapy for advanced disease who were treated with docetaxel 75 mg/m^2in combination with cisplatin and fluorouracil (see Table 10).

Table 10: Clinically Important Treatment-Emergent Adverse Reactions Regardless of Relationship to Treatment in the Gastric Cancer Study
 | Docetaxel 75 mg/m^2+ cisplatin 75 mg/m^2+ fluorouracil 750 mg/m^2 n=221 |  | Cisplatin 100 mg/m^2+ fluorouracil 1000 mg/m^2 n=224
Adverse Reaction | Any % | Grade 3/4 % | Any % | Grade 3/4 %
Anemia | 97 | 18 | 93 | 26
Neutropenia | 96 | 82 | 83 | 57
Fever in the absence of infection | 36 | 2 | 23 | 1
Thrombocytopenia | 26 | 8 | 39 | 14
Infection | 29 | 16 | 23 | 10
Febrile neutropenia | 16 | N/A | 5 | N/A
Neutropenic infection | 16 | N/A | 10 | N/A
Allergic reactions | 10 | 2 | 6 | 0
Fluid retention [Related to treatment] | 15 | 0 | 4 | 0
Edema | 13 | 0 | 3 | 0
Lethargy | 63 | 21 | 58 | 18
Neurosensory | 38 | 8 | 25 | 3
Neuromotor | 9 | 3 | 8 | 3
Dizziness | 16 | 5 | 8 | 2
Alopecia | 67 | 5 | 41 | 1
Rash/itch | 12 | 1 | 9 | 0
Nail changes | 8 | 0 | 0 | 0
Skin desquamation | 2 | 0 | 0 | 0
Nausea | 73 | 16 | 76 | 19
Vomiting | 67 | 15 | 73 | 19
Anorexia | 51 | 13 | 54 | 12
Stomatitis | 59 | 21 | 61 | 27
Diarrhea | 78 | 20 | 50 | 8
Constipation | 25 | 2 | 34 | 3
Esophagitis/dysphagia/odynophagia | 16 | 2 | 14 | 5
Gastrointestinal pain/cramping | 11 | 2 | 7 | 3
Cardiac dysrhythmias | 5 | 2 | 2 | 1
Myocardial ischemia | 1 | 0 | 3 | 2
Tearing | 8 | 0 | 2 | 0
Altered hearing | 6 | 0 | 13 | 2
Clinically important treatment emergent adverse reactions were determined based upon frequency, severity, and clinical impact of the adverse reaction.

Head and Neck Cancer

Combination therapy with docetaxel in head and neck cancer

Table 11summarizes the safety data obtained from patients that received induction chemotherapy with docetaxel 75 mg/m^2in combination with cisplatin and fluorouracil followed by radiotherapy (TAX323; 174 patients) or chemoradiotherapy (TAX324; 251 patients). The treatment regimens are described in Section 14.6.

Table 11: Clinically Important Treatment-Emergent Adverse Reactions (Regardless of Relationship) in Patients with SCCHN Receiving Induction Chemotherapy with Docetaxel in Combination with Cisplatin and Fluorouracil Followed by Radiotherapy (TAX323) or Chemoradiotherapy (TAX324)
 | TAX323 (n=355) |  |  |  | TAX324 (n=494)
 | Docetaxel arm (n=174) |  | Comparator arm (n=181) |  | Docetaxel arm (n=251) |  | Comparator arm (n=243)
Adverse Reaction (by Body System) | Any % | Grade 3/4 % | Any % | Grade 3/4 % | Any % | Grade 3/4 % | Any % | Grade 3/4 %
Neutropenia | 93 | 76 | 87 | 53 | 95 | 84 | 84 | 56
Anemia | 89 | 9 | 88 | 14 | 90 | 12 | 86 | 10
Thrombocytopenia | 24 | 5 | 47 | 18 | 28 | 4 | 31 | 11
Infection | 27 | 9 | 26 | 8 | 23 | 6 | 28 | 5
Febrile neutropenia [Febrile neutropenia: grade ≥2 fever concomitant with grade 4 neutropenia requiring intravenous antibiotics and/or hospitalization.] | 5 | N/A | 2 | N/A | 12 | N/A | 7 | N/A
Neutropenic infection | 14 | N/A | 8 | N/A | 12 | N/A | 8 | N/A
Cancer pain | 21 | 5 | 16 | 3 | 17 | 9 | 20 | 11
Lethargy | 41 | 3 | 38 | 3 | 61 | 5 | 56 | 10
Fever in the absence of infection | 32 | 1 | 37 | 0 | 30 | 4 | 28 | 3
Myalgia | 10 | 1 | 7 | 0 | 7 | 0 | 7 | 2
Weight loss | 21 | 1 | 27 | 1 | 14 | 2 | 14 | 2
Allergy | 6 | 0 | 3 | 0 | 2 | 0 | 0 | 0
Fluid retention [Related to treatment.] | 20 | 0 | 14 | 1 | 13 | 1 | 7 | 2
Edema only | 13 | 0 | 7 | 0 | 12 | 1 | 6 | 1
Weight gain only | 6 | 0 | 6 | 0 | 0 | 0 | 1 | 0
Dizziness | 2 | 0 | 5 | 1 | 16 | 4 | 15 | 2
Neurosensory | 18 | 1 | 11 | 1 | 14 | 1 | 14 | 0
Altered hearing | 6 | 0 | 10 | 3 | 13 | 1 | 19 | 3
Neuromotor | 2 | 1 | 4 | 1 | 9 | 0 | 10 | 2
Alopecia | 81 | 11 | 43 | 0 | 68 | 4 | 44 | 1
Rash/itch | 12 | 0 | 6 | 0 | 20 | 0 | 16 | 1
Dry skin | 6 | 0 | 2 | 0 | 5 | 0 | 3 | 0
Desquamation | 4 | 1 | 6 | 0 | 2 | 0 | 5 | 0
Nausea | 47 | 1 | 51 | 7 | 77 | 14 | 80 | 14
Stomatitis | 43 | 4 | 47 | 11 | 66 | 21 | 68 | 27
Vomiting | 26 | 1 | 39 | 5 | 56 | 8 | 63 | 10
Diarrhea | 33 | 3 | 24 | 4 | 48 | 7 | 40 | 3
Constipation | 17 | 1 | 16 | 1 | 27 | 1 | 38 | 1
Anorexia | 16 | 1 | 25 | 3 | 40 | 12 | 34 | 12
Esophagitis/dysphagia/ Odynophagia | 13 | 1 | 18 | 3 | 25 | 13 | 26 | 10
Taste, sense of smell altered | 10 | 0 | 5 | 0 | 20 | 0 | 17 | 1
Gastrointestinal pain/cramping | 8 | 1 | 9 | 1 | 15 | 5 | 10 | 2
Heartburn | 6 | 0 | 6 | 0 | 13 | 2 | 13 | 1
Gastrointestinal bleeding | 4 | 2 | 0 | 0 | 5 | 1 | 2 | 1
Cardiac dysrhythmia | 2 | 2 | 2 | 1 | 6 | 3 | 5 | 3
Venous [Includes superficial and deep vein thrombosis and pulmonary embolism] | 3 | 2 | 6 | 2 | 4 | 2 | 5 | 4
Ischemia myocardial | 2 | 2 | 1 | 0 | 2 | 1 | 1 | 1
Tearing | 2 | 0 | 1 | 0 | 2 | 0 | 2 | 0
Conjunctivitis | 1 | 0 | 1 | 0 | 1 | 0 | 0.4 | 0
Clinically important treatment-emergent adverse reactions based upon frequency, severity, and clinical impact.

6.2 Postmarketing Experience

The following adverse reactions have been identified from clinical trials and/or postmarketing surveillance. Because these reactions are reported from a population of uncertain size, it is not always possible to reliably estimate their frequency or establish a causal relationship to drug exposure.

Body as a whole: diffuse pain, chest pain, radiation recall phenomenon, injection site recall reaction (recurrence of skin reaction at a site of previous extravasation following administration of docetaxel at a different site) at the site of previous extravasation.

Cardiovascular: atrial fibrillation, deep vein thrombosis, ECG abnormalities, thrombophlebitis, pulmonary embolism, syncope, tachycardia, myocardial infarction. Ventricular arrhythmia, including ventricular tachycardia, in patients treated with docetaxel in combination regimens including doxorubicin, 5-fluorouracil and/or cyclophosphamide may be associated with fatal outcome.

Cutaneous: cutaneous lupus erythematosus, bullous eruptions such as erythema multiforme and severe cutaneous adverse reactions (SCARs) such as Stevens-Johnson syndrome, toxic epidermal necrolysis and acute generalized exanthematous pustulosis, scleroderma-like changes (usually preceded by peripheral lymphedema), severe palmar-plantar erythrodysesthesia, and permanent alopecia.

Gastrointestinal: enterocolitis, including colitis, ischemic colitis, and neutropenic enterocolitis, which may be fatal. Abdominal pain, anorexia, constipation, duodenal ulcer, esophagitis, gastrointestinal hemorrhage, gastrointestinal perforation, intestinal obstruction, ileus, and dehydration as a consequence of gastrointestinal events.

Hearing: ototoxicity, hearing disorders and/or hearing loss, including during use with other ototoxic drugs.

Hematologic: bleeding episodes, disseminated intravascular coagulation (DIC), often in association with sepsis or multiorgan failure.

Hepatic: hepatitis, sometimes fatal, primarily in patients with pre-existing liver disorders.

Hypersensitivity: anaphylactic shock with fatal outcome in patients who received premedication. Severe hypersensitivity reactions with fatal outcome with docetaxel in patients who previously experienced hypersensitivity reactions to paclitaxel.

Metabolism and nutrition disorders: electrolyte imbalance, including hyponatremia, hypokalemia, hypomagnesemia, and hypocalcemia. Tumor lysis syndrome, sometimes fatal.

Neurologic: confusion, seizures or transient loss of consciousness, sometimes appearing during the infusion of the drug.

Ophthalmologic: conjunctivitis, lacrimation or lacrimation with or without conjunctivitis, cystoid macular edema (CME). Excessive tearing which may be attributable to lacrimal duct obstruction. Transient visual disturbances (flashes, flashing lights, scotomata), typically occurring during drug infusion and reversible upon discontinuation of the infusion, in association with hypersensitivity reactions.

Respiratory: dyspnea, acute pulmonary edema, acute respiratory distress syndrome/pneumonitis, interstitial lung disease, interstitial pneumonia, respiratory failure, and pulmonary fibrosis, which may be fatal. Radiation pneumonitis in patients receiving concomitant radiotherapy.

Renal: renal insufficiency and renal failure, the majority of cases were associated with concomitant nephrotoxic drugs.

Second primary malignancies: second primary malignancies, including AML, MDS, NHL, and renal cancer [see Warnings and Precautions (5.7)].

Musculoskeletal disorder: myositis.

7 DRUG INTERACTIONS

Docetaxel is a CYP3A4 substrate. In vitrostudies have shown that the metabolism of docetaxel may be modified by the concomitant administration of compounds that induce, inhibit, or are metabolized by cytochrome P450 3A4.

In vivostudies showed that the exposure of docetaxel increased 2.2-fold when it was coadministered with ketoconazole, a potent inhibitor of CYP3A4. Protease inhibitors, particularly ritonavir, may increase the exposure of docetaxel. Concomitant use of Docetaxel Injection and drugs that inhibit CYP3A4 may increase exposure to docetaxel and should be avoided. In patients receiving treatment with Docetaxel Injection, close monitoring for toxicity and a Docetaxel Injection dose reduction could be considered if systemic administration of a potent CYP3A4 inhibitor cannot be avoided [see Dosage and Administration (2.7), Clinical Pharmacology (12.3)].

8 USE IN SPECIFIC POPULATIONS

8.1 Pregnancy

Risk Summary

Based on findings in animal reproduction studies and its mechanism of action, Docetaxel Injection can cause fetal harm when administered to a pregnant woman [see Clinical Pharmacology (12.1)]. Available data from case reports in the literature and pharmacovigilance with docetaxel use in pregnant women are not sufficient to inform the drug-associated risk of major birth defects, miscarriage, or adverse maternal or fetal outcomes. Docetaxel Injection contains alcohol which can interfere with neurobehavioral development [see Clinical Considerations].In animal reproductive studies, administration of docetaxel to pregnant rats and rabbits during the period of organogenesis caused an increased incidence of embryo-fetal toxicities, including intrauterine mortality, at doses as low as 0.02 and 0.003 times the recommended human dose based on body surface area, respectively [see Data].Advise pregnant women and females of reproductive potential of the potential risk to a fetus.

The estimated background risk of major birth defects and miscarriage for the indicated populations is unknown. All pregnancies have a background risk of birth defect, miscarriage, or other adverse outcomes. In the U.S. general population, the estimated background risk of major birth defects and miscarriage in clinically recognized pregnancies is 2% to 4% and 15% to 20%, respectively.

Clinical Considerations

Docetaxel Injection contains alcohol [see Warnings and Precautions (5.13)]. Published studies have demonstrated that alcohol is associated with fetal harm including central nervous system abnormalities, behavioral disorders, and impaired intellectual development.

Data
Animal data

Intravenous administration of ≥0.3 and 0.03 mg/kg/day docetaxel to pregnant rats and rabbits, respectively, during the period of organogenesis caused an increased incidence of intrauterine mortality, resorptions, reduced fetal weights, and fetal ossification delays. Maternal toxicity was also observed at these doses, which were approximately 0.02 and 0.003 times the daily maximum recommended human dose based on body surface area, respectively.

8.2 Lactation

Risk Summary

There is no information regarding the presence of docetaxel in human milk, or on its effects on milk production or the breastfed child. No lactation studies in animals have been conducted. Because of the potential for serious adverse reactions in a breastfed child, advise women not to breastfeed during treatment with Docetaxel Injection and for 1 week after the last dose.

8.3 Females and Males of Reproductive Potential

Based on findings in animals, Docetaxel Injection can cause fetal harm when administered to a pregnant woman [see Use in Specific Populations (8.1)].

Pregnancy Testing

Verify pregnancy status in females of reproductive potential prior to initiating Docetaxel Injection.

Contraception

Females

Based on genetic toxicity findings, advise females of reproductive potential to use effective contraception during treatment and for 2 months after the last dose of Docetaxel Injection.

Males

Based on genetic toxicity findings, advise male patients with female partners of reproductive potential to use effective contraception during treatment and for 4 months after the last dose of Docetaxel Injection.

Infertility

Based on findings in animal studies, Docetaxel Injection may impair fertility in males of reproductive potential [see Nonclinical Toxicology (13.1)].

8.4 Pediatric Use

The alcohol content of Docetaxel Injection should be taken into account when given to pediatric patients [ see Warnings and Precautions (5.13)].

The efficacy of Docetaxel Injection in pediatric patients as monotherapy or in combination has not been established. The overall safety profile of Docetaxel Injection in pediatric patients receiving monotherapy or TCF was consistent with the known safety profile in adults.

Docetaxel Injection has been studied in a total of 289 pediatric patients: 239 in 2 trials with monotherapy and 50 in combination treatment with cisplatin and 5-fluorouracil (TCF).

Docetaxel Injection Monotherapy

Docetaxel Injection monotherapy was evaluated in a dose-finding phase 1 trial in 61 pediatric patients (median age 12.5 years, range 1-22 years) with a variety of refractory solid tumors. The recommended dose was 125 mg/m^2as a 1-hour intravenous infusion every 21 days. The primary dose limiting toxicity was neutropenia.

The recommended dose for Docetaxel Injection monotherapy was evaluated in a phase 2 single-arm trial in 178 pediatric patients (median age 12 years, range 1-26 years) with a variety of recurrent/refractory solid tumors. Efficacy was not established with tumor response rates ranging from one complete response (CR) (0.6%) in a patient with undifferentiated sarcoma to four partial responses (2.2%) seen in one patient each with Ewing Sarcoma, neuroblastoma, osteosarcoma, and squamous cell carcinoma.

Docetaxel Injection in Combination

Docetaxel Injection was studied in combination with cisplatin and 5-fluorouracil (TCF) versus cisplatin and 5-fluorouracil (CF) for the induction treatment of nasopharyngeal carcinoma (NPC) in pediatric patients prior to chemoradiation consolidation. Seventy-five patients (median age 16 years, range 9 to 21 years) were randomized (2:1) to Docetaxel Injection (75 mg/m^2) in combination with cisplatin (75 mg/m^2) and 5-fluorouracil (750 mg/m^2) (TCF) or to cisplatin (80 mg/m^2) and 5-fluorouracil (1000 mg/m^2/day) (CF). The primary endpoint was the CR rate following induction treatment of NPC. One patient out of 50 in the TCF group (2%) had a complete response while none of the 25 patients in the CF group had a complete response.

Pharmacokinetics

Pharmacokinetic parameters for docetaxel were determined in 2 pediatric solid tumor trials. Following docetaxel administration at 55 mg/m^2to 235 mg/m^2in a 1-hour intravenous infusion every 3 weeks in 25 patients aged 1 to 20 years (median 11 years), docetaxel clearance was 17.3±10.9 L/h/m^2.

Docetaxel was administered in combination with cisplatin and 5-fluorouracil (TCF), at dose levels of 75 mg/m^2in a 1-hour intravenous infusion day 1 in 28 patients aged 10 to 21 years (median 16 years, 17 patients were older than 16). Docetaxel clearance was 17.9±8.75 L/h/m^2, corresponding to an AUC of 4.20±2.57 μg∙h/mL.

In summary, the body surface area adjusted clearance of docetaxel monotherapy and TCF combination in children were comparable to those in adults [ see Clinical Pharmacology (12.3)].

8.5 Geriatric Use

In general, dose selection for an elderly patient should be cautious, reflecting the greater frequency of decreased hepatic, renal, or cardiac function and of concomitant disease or other drug therapy in elderly patients.

Non-small Cell Lung Cancer

In a study conducted in chemotherapy-naive patients with NSCLC (TAX326), 148 patients (36%) in the docetaxel+cisplatin group were 65 years of age or greater. There were 128 patients (32%) in the vinorelbine+cisplatin group 65 years of age or greater. In the docetaxel+cisplatin group, patients less than 65 years of age had a median survival of 10.3 months (95% CI: 9.1 months, 11.8 months) and patients 65 years or older had a median survival of 12.1 months (95% CI: 9.3 months, 14 months). In patients 65 years of age or greater treated with docetaxel+cisplatin, diarrhea (55%), peripheral edema (39%) and stomatitis (28%) were observed more frequently than in the vinorelbine+cisplatin group (diarrhea 24%, peripheral edema 20%, stomatitis 20%). Patients treated with docetaxel+cisplatin who were 65 years of age or greater were more likely to experience diarrhea (55%), infections (42%), peripheral edema (39%) and stomatitis (28%) compared to patients less than the age of 65 administered the same treatment (43%, 31%, 31% and 21%, respectively).

When docetaxel was combined with carboplatin for the treatment of chemotherapy-naive, advanced non-small cell lung carcinoma, patients 65 years of age or greater (28%) experienced higher frequency of infection compared to similar patients treated with docetaxel+cisplatin, and a higher frequency of diarrhea, infection and peripheral edema than elderly patients treated with vinorelbine+cisplatin.

Prostate Cancer

Of the 333 patients treated with docetaxel every three weeks plus prednisone in the prostate cancer study (TAX327), 209 patients were 65 years of age or greater and 68 patients were older than 75 years. In patients treated with docetaxel every three weeks, the following treatment-emergent adverse reactions occurred at rates ≥10% higher in patients 65 years of age or greater compared to younger patients: anemia (71% vs 59%), infection (37% vs 24%), nail changes (34% vs 23%), anorexia (21% vs 10%), weight loss (15% vs 5%), respectively.

Breast Cancer

In the adjuvant breast cancer trial (TAX316), docetaxel in combination with doxorubicin and cyclophosphamide was administered to 744 patients of whom 48 (6%) were 65 years of age or greater. The number of elderly patients who received this regimen was not sufficient to determine whether there were differences in safety and efficacy between elderly and younger patients.

Gastric Cancer

Among the 221 patients treated with docetaxel in combination with cisplatin and fluorouracil in the gastric cancer study, 54 were 65 years of age or older and 2 patients were older than 75 years. In this study, the number of patients who were 65 years of age or older was insufficient to determine whether they respond differently from younger patients. However, the incidence of serious adverse reactions was higher in the elderly patients compared to younger patients. The incidence of the following adverse reactions (all grades, regardless of relationship): lethargy, stomatitis, diarrhea, dizziness, edema, febrile neutropenia/neutropenic infection occurred at rates ≥ 10% higher in patients who were 65 years of age or older compared to younger patients. Elderly patients treated with TCF should be closely monitored.

Head and Neck Cancer

Among the 174 and 251 patients who received the induction treatment with docetaxel in combination with cisplatin and fluorouracil (TPF) for SCCHN in the TAX323 and TAX324 studies, 18 (10%) and 32 (13%) of the patients were 65 years of age or older, respectively.

These clinical studies of docetaxel in combination with cisplatin and fluorouracil in patients with SCCHN did not include sufficient numbers of patients aged 65 and over to determine whether they respond differently from younger patients. Other reported clinical experience with this treatment regimen has not identified differences in responses between elderly and younger patients.

8.6 Hepatic Impairment

Avoid Docetaxel Injection in patients with bilirubin >ULN and patients with AST and/or ALT >1.5 × ULN concomitant with alkaline phosphatase >2.5 × ULN [see Boxed Warning, Warnings and Precautions (5.2), Clinical Pharmacology (12.3)].

The alcohol content of Docetaxel Injection should be taken into account when given to patients with hepatic impairment [ see Warnings and Precautions (5.13)].

10 OVERDOSAGE

There is no known antidote for Docetaxel Injection overdosage. In case of overdosage, the patient should be kept in a specialized unit where vital functions can be closely monitored. Anticipated complications of overdosage include: bone marrow suppression, peripheral neurotoxicity, and mucositis. Patients should receive therapeutic G-CSF as soon as possible after discovery of overdose. Other appropriate symptomatic measures should be taken, as needed.

In two reports of overdose, one patient received 150 mg/m^2and the other received 200 mg/m^2as 1-hour infusions. Both patients experienced severe neutropenia, mild asthenia, cutaneous reactions, and mild paresthesia, and recovered without incident.

In mice, lethality was observed following single intravenous doses that were ≥154 mg/kg (about 4.5 times the human dose of 100 mg/m^2on a mg/m^2basis); neurotoxicity associated with paralysis, non-extension of hind limbs, and myelin degeneration was observed in mice at 48 mg/kg (about 1.5 times the human dose of 100 mg/m^2basis). In male and female rats, lethality was observed at a dose of 20 mg/kg (comparable to the human dose of 100 mg/m^2on a mg/m^2basis) and was associated with abnormal mitosis and necrosis of multiple organs.

11 DESCRIPTION

Docetaxel is an antineoplastic agent belonging to the taxoid family. It is prepared by semisynthesis beginning with a precursor extracted from the renewable needle biomass of yew plants. The chemical name for docetaxel is (2R,3S)-N-carboxy-3-phenylisoserine,N- tert-butyl ester, 13-ester with 5β-20-epoxy-1,2α,4,7β,10β,13α-hexahydroxytax-11-en-9-one 4-acetate 2-benzoate. Docetaxel has the following structural formula:

Docetaxel is a white to off-white powder with an empirical formula of C43H53NO14, and a molecular weight of 807.88. It is highly lipophilic and practically insoluble in water.

One-vial Docetaxel Injection

Docetaxel Injection USP is a sterile, non-pyrogenic, pale-yellow to brownish-yellow solution at 20 mg/mL concentration.

Each mL contains 20 mg docetaxel anhydrous USP, in 4 mg anhydrous citric acid for pH adjustment, 520 mg polysorbate 80 and 395 mg dehydrated alcohol solution.

Docetaxel Injection USP is available in multiple dose (20 mg/mL, 80 mg/4 mL and 160 mg/8 mL) vials containing 20 mg (1 mL), 80 mg (4 mL) or 160 mg (8 mL) docetaxel anhydrous USP.

Docetaxel Injection USP requires NO prior dilution with a diluent and is ready to add to the infusion solution.

12 CLINICAL PHARMACOLOGY

12.1 Mechanism of Action

Docetaxel is an antineoplastic agent that acts by disrupting the microtubular network in cells that is essential for mitotic and interphase cellular functions. Docetaxel binds to free tubulin and promotes the assembly of tubulin into stable microtubules while simultaneously inhibiting their disassembly. This leads to the production of microtubule bundles without normal function and to the stabilization of microtubules, which results in the inhibition of mitosis in cells. Docetaxel’s binding to microtubules does not alter the number of protofilaments in the bound microtubules, a feature which differs from most spindle poisons currently in clinical use.

12.3 Pharmacokinetics

Absorption
The pharmacokinetics of docetaxel has been evaluated in cancer patients after administration of 20 mg/m^2to 115 mg/m^2in phase 1 studies. The area under the curve (AUC) was dose proportional following doses of 70 mg/m^2to 115 mg/m^2with infusion times of 1 to 2 hours. Docetaxel’s pharmacokinetic profile is consistent with a three-compartment pharmacokinetic model, with initial rapid distribution phase and the late (terminal) phase.

Distribution
Mean steady state volume of distribution was 113 L. Docetaxel is approximately 94% protein bound in vitro, mainly to α1-acid glycoprotein, albumin, and lipoproteins. In three cancer patients, the in vitro binding to plasma proteins was approximately 97%. Dexamethasone does not affect the protein binding of docetaxel.

Elimination
With extended plasma sampling up to 8 to 22 days post infusion, the estimated mean total body clearance was 18 L/h/ m^2(range of means: 14 to 23) and mean terminal elimination half-life was 116 hours (range of means: 92 to 135).

Metabolism
Docetaxel is metabolized by the CYP3A4 isoenzyme in vitro [see Drug Interactions (7)].

Excretion
In three cancer patients urinary and fecal excretion accounted for approximately 6% and 75% of the administered radioactivity, respectively, within 7 days. About 80% of the radioactivity recovered in feces was excreted during the first 48 hours as 1 major and 3 minor metabolites with less than 8% as unchanged drug.

Specific Populations
Effect of Age: A population pharmacokinetic analysis was carried out after docetaxel treatment of 535 patients dosed at 100 mg/m^2. Pharmacokinetic parameters estimated by this analysis were very close to those estimated from phase 1 studies. The pharmacokinetics of docetaxel was not influenced by age.

Effect of Gender: The population pharmacokinetics analysis described above also indicated that gender did not influence the pharmacokinetics of docetaxel.

Hepatic Impairment: The population pharmacokinetic analysis described above indicated that in patients with clinical chemistry data suggestive of mild to moderate liver impairment (AST and/or ALT >1.5 times ULN concomitant with alkaline phosphatase >2.5 times ULN), total body clearance was lowered by an average of 27%, resulting in a 38% increase in systemic exposure (AUC). This average, however, includes a substantial range and there is, at present, no measurement that would allow recommendation for dose adjustment in such patients. Patients with combined abnormalities of transaminase and alkaline phosphatase should not be treated with Docetaxel Injection. Patients with severe hepatic impairment have not been studied [see Warnings and Precautions (5.2), Use in Specific Populations (8.6)].

Effect of Race: Mean total body clearance for Japanese patients dosed at the range of 10 mg/m^2to 90 mg/m^2was similar to that of European/American populations dosed at 100 mg/m^2, suggesting no significant difference in the elimination of docetaxel in the two populations.

Drug Interaction Studies
Effect of Ketoconazole: The effect of ketoconazole (a strong CYP3A4 inhibitor) on the pharmacokinetics of docetaxel was investigated in 7 cancer patients. Patients were randomized to receive either docetaxel (100 mg/m^2intravenous) alone or docetaxel (10 mg/m^2intravenous) in combination with ketoconazole (200 mg orally once daily for 3 days) in a crossover design with a 3-week washout period. The results of this study indicated that the mean dose-normalized AUC of docetaxel was increased 2.2-fold and its clearance was reduced by 49% when docetaxel was coadministered with ketoconazole [see Dosage and Administration (2.7), Drug Interactions (7)]

Effect of combination therapies

- Dexamethasone: Docetaxel total body clearance was not modified by pretreatment with dexamethasone.
- Cisplatin: Clearance of docetaxel in combination therapy with cisplatin was similar to that previously observed following monotherapy with docetaxel. The pharmacokinetic profile of cisplatin in combination therapy with docetaxel was similar to that observed with cisplatin alone.
- Cisplatin and Fluorouracil: The combined administration of docetaxel, cisplatin and fluorouracil in 12 patients with solid tumors had no influence on the pharmacokinetics of each individual drug.
- Prednisone: A population pharmacokinetic analysis of plasma data from 40 patients with metastatic castration-resistant prostate cancer indicated that docetaxel systemic clearance in combination with prednisone is similar to that observed following administration of docetaxel alone.
- Cyclophosphamide and Doxorubicin: A study was conducted in 30 patients with advanced breast cancer to determine the potential for drug-drug interactions between docetaxel (75 mg/m^2), doxorubicin (50 mg/m^2), and cyclophosphamide (500 mg/m^2) when administered in combination. The coadministration of docetaxel had no effect on the pharmacokinetics of doxorubicin and cyclophosphamide when the three drugs were given in combination compared to coadministration of doxorubicin and cyclophosphamide only. In addition, doxorubicin and cyclophosphamide had no effect on docetaxel plasma clearance when the three drugs were given in combination compared to historical data for docetaxel monotherapy.

13 NONCLINICAL TOXICOLOGY

13.1 Carcinogenesis, Mutagenesis, Impairment of Fertility

Carcinogenicity studies with docetaxel have not been performed.

Docetaxel was genotoxic by an aneugenic mechanism in the in vitrochromosome aberration test in CHO-K1cells and in the in vivomicronucleus test in mice administered doses of 0.39 to 1.56 mg/kg (about 1/60thto 1/15ththe recommended human dose on a mg/m^2basis). Docetaxel was not mutagenic in the Ames test or the CHO/HGPRT gene mutation assays.

Docetaxel did not reduce fertility in rats when administered in multiple intravenous doses of up to 0.3 mg/kg (about 1/50ththe recommended human dose on a mg/m^2basis), but decreased testicular weights were reported. This correlates with findings of a 10-cycle toxicity study (dosing once every 21 days for 6 months) in rats and dogs in which testicular atrophy or degeneration was observed at intravenous doses of 5 mg/kg in rats and 0.375 mg/kg in dogs (about 1/3rdand 1/15ththe recommended human dose on a mg/m^2basis, respectively). An increased frequency of dosing in rats produced similar effects at lower dose levels.

14 CLINICAL STUDIES

14.1 Locally Advanced or Metastatic Breast Cancer

The efficacy and safety of docetaxel have been evaluated in locally advanced or metastatic breast cancer after failure of previous chemotherapy (alkylating agent-containing regimens or anthracycline-containing regimens).

Randomized Trials

In one randomized trial, patients with a history of prior treatment with an anthracycline containing regimen were assigned to treatment with docetaxel (100 mg/m^2every 3 weeks) or the combination of mitomycin (12 mg/m^2every 6 weeks) and vinblastine (6 mg/m^2every 3 weeks). Two hundred three patients were randomized to docetaxel and 189 to the comparator arm. Most patients had received prior chemotherapy for metastatic disease; only 27 patients on the docetaxel arm and 33 patients on the comparator arm entered the study following relapse after adjuvant therapy. Three-quarters of patients had measurable, visceral metastases. The primary endpoint was time to progression. The following table summarizes the study results (See Table 12.)

Table 12: Efficacy of Docetaxel in the Treatment of Breast Cancer Patients Previously Treated with an Anthracycline-Containing Regimen (Intent-to-Treat Analysis)
Efficacy Parameter | Docetaxel (n=203) | Mitomycin/Vinblastine (n=189) | p-value
Median Survival | 11.4 months | 8.7 months
Risk Ratio [For the risk ratio, a value less than 1.00 favors docetaxel.] , Mortality (Docetaxel: Control) | 0.73 |  | p=0.01 Log Rank
 |  |  | p=0.01 Log Rank
95% CI (Risk Ratio) | 0.58-0.93 |  | p=0.01 Log Rank
Median Time to Progression | 4.3 months | 2.5 months
Risk Ratio , Progression (Docetaxel: Control) | 0.75 |  | p=0.01 Log Rank
 |  |  | p=0.01 Log Rank
95% CI (Risk Ratio) | 0.61-0.94 |  | p=0.01 Log Rank
Overall Response Rate | 28.1% | 9.5% | p<0.0001
Complete Response Rate | 3.4% | 1.6% | Chi Square

In a second randomized trial, patients previously treated with an alkylating-containing regimen were assigned to treatment with docetaxel (100 mg/m^2) or doxorubicin (75 mg/m^2) every 3 weeks. One hundred sixty-one patients were randomized to docetaxel and 165 patients to doxorubicin. Approximately one-half of patients had received prior chemotherapy for metastatic disease, and one-half entered the study following relapse after adjuvant therapy. Three-quarters of patients had measurable, visceral metastases. The primary endpoint was time to progression. The study results are summarized below (See Table 13.)

Table 13: Efficacy of Docetaxel in the Treatment of Breast Cancer Patients Previously Treated with an Alkylating-Containing Regimen (Intent-to-Treat Analysis)
Efficacy Parameter | Docetaxel (n=161) | Doxorubicin (n=165) | p-value
Median Survival | 14.7 months | 14.3 months
Risk Ratio [For the risk ratio, a value less than 1.00 favors docetaxel.] , Mortality (Docetaxel: Control) | 0.89 |  | p=0.39 Log Rank
 |  |  | p=0.39 Log Rank
95% CI (Risk Ratio) | 0.68-1.16 |  | p=0.39 Log Rank
Median Time to Progression | 6.5 months | 5.3 months
Risk Ratio , Progression (Docetaxel: Control) | 0.93 |  | p=0.45 Log Rank
 |  |  | p=0.45 Log Rank
95% CI (Risk Ratio) | 0.71-1.16 |  | p=0.45 Log Rank
Overall Response Rate | 45.3% | 29.7% | p=0.004
Complete Response Rate | 6.8% | 4.2% | Chi Square

In another multicenter open-label, randomized trial (TAX313), in the treatment of patients with advanced breast cancer who progressed or relapsed after one prior chemotherapy regimen, 527 patients were randomized to receive docetaxel monotherapy 60 mg/m^2(n=151), 75 mg/m^2(n=188) or 100 mg/m^2(n=188). In this trial, 94% of patients had metastatic disease and 79% had received prior anthracycline therapy. Response rate was the primary endpoint. Response rates increased with docetaxel dose: 19.9% for the 60 mg/m^2group compared to 22.3% for the 75 mg/m^2and 29.8% for the 100 mg/m^2group; pair-wise comparison between the 60 mg/m^2and 100 mg/m^2groups was statistically significant (p=0.037).

Single Arm Studies

Docetaxel at a dose of 100 mg/m^2was studied in six single arm studies involving a total of 309 patients with metastatic breast cancer in whom previous chemotherapy had failed. Among these, 190 patients had anthracycline-resistant breast cancer, defined as progression during an anthracycline-containing chemotherapy regimen for metastatic disease, or relapse during an anthracycline-containing adjuvant regimen. In anthracycline-resistant patients, the overall response rate was 37.9% (72/190; 95% CI: 31.0-44.8) and the complete response rate was 2.1%.

Docetaxel was also studied in three single arm Japanese studies at a dose of 60 mg/m^2, in 174 patients who had received prior chemotherapy for locally advanced or metastatic breast cancer. Among 26 patients whose best response to an anthracycline had been progression, the response rate was 34.6% (95% CI: 17.2-55.7), similar to the response rate in single arm studies of 100 mg/m^2.

14.2 Adjuvant Treatment of Breast Cancer

A multicenter, open-label, randomized trial (TAX316) evaluated the efficacy and safety of docetaxel for the adjuvant treatment of patients with axillary-node-positive breast cancer and no evidence of distant metastatic disease. After stratification according to the number of positive lymph nodes (1-3, 4+), 1491 patients were randomized to receive either docetaxel 75 mg/m^2administered 1-hour after doxorubicin 50 mg/m^2and cyclophosphamide 500 mg/m^2(TAC arm), or doxorubicin 50 mg/m^2followed by fluorouracil 500 mg/m^2and cyclophosphamide 500 mg/m^2(FAC arm). Both regimens were administered every 3 weeks for 6 cycles.

Docetaxel was administered as a 1-hour infusion; all other drugs were given as intravenous bolus on day 1. In both arms, after the last cycle of chemotherapy, patients with positive estrogen and/or progesterone receptors received tamoxifen 20 mg daily for up to 5 years. Adjuvant radiation therapy was prescribed according to guidelines in place at participating institutions and was given to 69% of patients who received TAC and 72% of patients who received FAC.

Results from a second interim analysis (median follow-up 55 months) are as follows: In study TAX316, the docetaxel-containing combination regimen TAC showed significantly longer disease-free survival (DFS) than FAC (hazard ratio=0.74; 2-sided 95% CI=0.60, 0.92, stratified log rank p=0.0047). The primary endpoint, disease-free survival, included local and distant recurrences, contralateral breast cancer and deaths from any cause. The overall reduction in risk of relapse was 25.7% for TAC-treated patients. (See Figure 1.)

At the time of this interim analysis, based on 219 deaths, overall survival was longer for TAC than FAC (hazard ratio=0.69, 2-sided 95% CI=0.53, 0.90). (See Figure 2.) There will be further analysis at the time survival data mature.

Figure 1: TAX316 Disease Free Survival K-M curve

Figure 2: TAX316 Overall Survival K-M curve

The following table describes the results of subgroup analyses for DFS and OS (see Table 14).

Table 14: Subset Analyses-Adjuvant Breast Cancer Study
 |  | Disease Free Survival |  | Overall Survival
Patient subset | Number of patients | Hazard ratio [a hazard ratio of less than 1 indicates that TAC is associated with a longer disease free survival or overall survival compared to FAC.] | 95% CI | Hazard ratio | 95% CI
No. of positive nodes
Overall | 744 | 0.74 | (0.60, 0.92) | 0.69 | (0.53, 0.90)
1-3 | 467 | 0.64 | (0.47, 0.87) | 0.45 | (0.29, 0.70)
4+ | 277 | 0.84 | (0.63, 1.12) | 0.93 | (0.66, 1.32)
Receptor status
Positive | 566 | 0.76 | (0.59, 0.98) | 0.69 | (0.48, 0.99)
Negative | 178 | 0.68 | (0.48, 0.97) | 0.66 | (0.44, 0.98)

14.3 Non-small Cell Lung Cancer (NSCLC)

The efficacy and safety of docetaxel has been evaluated in patients with unresectable, locally advanced or metastatic non-small cell lung cancer whose disease has failed prior platinum-based chemotherapy or in patients who are chemotherapy naive.

Monotherapy with docetaxel for NSCLC Previously Treated with Platinum-Based Chemotherapy

Two randomized, controlled trials established that a docetaxel dose of 75 mg/m^2was tolerable and yielded a favorable outcome in patients previously treated with platinum-based chemotherapy (see below). Docetaxel at a dose of 100 mg/m^2, however, was associated with unacceptable hematologic toxicity, infections, and treatment-related mortality and this dose should not be used [see Boxed Warning, Dosage and Administration (2.7), Warnings and Precautions (5.3)].

One trial (TAX317), randomized patients with locally advanced or metastatic non-small cell lung cancer, a history of prior platinum-based chemotherapy, no history of taxane exposure, and an ECOG performance status ≤2 to docetaxel or best supportive care. The primary endpoint of the study was survival. Patients were initially randomized to docetaxel 100 mg/m^2or best supportive care, but early toxic deaths at this dose led to a dose reduction to docetaxel 75 mg/m^2. A total of 104 patients were randomized in this amended study to either docetaxel 75 mg/m^2or best supportive care.

In a second randomized trial (TAX320), 373 patients with locally advanced or metastatic non-small cell lung cancer, a history of prior platinum-based chemotherapy, and an ECOG performance status ≤2 were randomized to docetaxel 75 mg/m^2, docetaxel 100 mg/m^2and a treatment in which the investigator chose either vinorelbine 30 mg/m^2days 1, 8, and 15 repeated every 3 weeks or ifosfamide 2 g/m^2days 1-3 repeated every 3 weeks. Forty percent of the patients in this study had a history of prior paclitaxel exposure. The primary endpoint was survival in both trials. The efficacy data for the docetaxel 75 mg/m^2arm and the comparator arms are summarized in Table 15 and Figures 3 and 4 showing the survival curves for the two studies.

Table 15 : Efficacy of Docetaxel in the Treatment of Non-Small Cell Lung Cancer Patients Previously Treated with a Platinum-Based Chemotherapy Regimen (Intent-to-Treat Analysis)
 | TAX317 |  | TAX320
 | Docetaxel 75 mg/m^2 n=55 | Best Supportive Care n=49 | Docetaxel 75 mg/m^2 n=125 | Control (V/I [Vinorelbine/Ifosfamide]) n=123
Overall Survival
Log-rank Test | p=0.01 |  | p=0.13
Risk Ratio [a value less than 1.00 favors docetaxel] , Mortality
(Docetaxel: Control) | 0.56 |  | 0.82
95% CI (Risk Ratio) | (0.35, 0.88) |  | (0.63, 1.06)
Median Survival | 7.5 months [p≤0.05] | 4.6 months | 5.7 months | 5.6 months
95% CI | (5.5, 12.8) | (3.7, 6.1) | (5.1, 7.1) | (4.4, 7.9)
% 1-year Survival | 37% [uncorrected for multiple comparisons] | 12% | 30% | 20%
95% CI | (24, 50) | (2, 23) | (22, 39) | (13, 27)
Time to Progression | 12.3 weeks | 7.0 weeks | 8.3 weeks | 7.6 weeks
95% CI | (9.0, 18.3) | (6.0, 9.3) | (7.0, 11.7) | (6.7, 10.1)
Response Rate | 5.5% | Not Applicable | 5.7% | 0.8%
95% CI | (1.1, 15.1) |  | (2.3, 11.3) | (0.0, 4.5)

Only one of the two trials (TAX317) showed a clear effect on survival, the primary endpoint; that trial also showed an increased rate of survival to one year. In the second study (TAX320) the rate of survival at one year favored docetaxel 75 mg/m^2.

Figure 3: TAX317 Survival K-M Curves - Docetaxel 75 mg/m^2Versus Best Supportive Care

Figure 4: TAX320 Survival K-M Curves - Docetaxel 75 mg/m^2Versus Vinorelbine or Ifosfamide Control

Patients treated with docetaxel at a dose of 75 mg/m^2experienced no deterioration in performance status and body weight relative to the comparator arms used in these trials.

Combination Therapy with docetaxel for Chemotherapy-Naive NSCLC

In a randomized controlled trial (TAX326), 1218 patients with unresectable stage IIIB or IV NSCLC and no prior chemotherapy were randomized to receive one of three treatments: docetaxel 75 mg/m^2as a 1 hour infusion immediately followed by cisplatin 75 mg/m^2over 30 to 60 minutes every 3 weeks; vinorelbine 25 mg/m^2administered over 6-10 minutes on days 1, 8, 15, 22 followed by cisplatin 100 mg/m^2administered on day 1 of cycles repeated every 4 weeks; or a combination of docetaxel and carboplatin.

The primary efficacy endpoint was overall survival. Treatment with docetaxel+cisplatin did not result in a statistically significantly superior survival compared to vinorelbine+cisplatin (see table below). The 95% confidence interval of the hazard ratio (adjusted for interim analysis and multiple comparisons) shows that the addition of docetaxel to cisplatin results in an outcome ranging from a 6% inferior to a 26% superior survival compared to the addition of vinorelbine to cisplatin. The results of a further statistical analysis showed that at least (the lower bound of the 95% confidence interval) 62% of the known survival effect of vinorelbine when added to cisplatin (about a 2-month increase in median survival; Wozniak et al. JCO, 1998) was maintained. The efficacy data for the docetaxel+cisplatin arm and the comparator arm are summarized in Table 16.

Table 16: Survival Analysis of Docetaxel in Combination Therapy for Chemotherapy-Naive NSCLC
Comparison | Docetaxel + Cisplatin n=408 | Vinorelbine + Cisplatin n=405
Kaplan-Meier Estimate of Median Survival | 10.9 months | 10.0 months
p-value [From the superiority test (stratified log rank) comparing docetaxel + cisplatin to vinorelbine+cisplatin] | 0.122
Estimated Hazard Ratio [Hazard ratio of docetaxel + cisplatin vs. vinorelbine + cisplatin. A hazard ratio of less than 1 indicates that docetaxel + cisplatin is associated with a longer survival.] | 0.88
Adjusted 95% CI [Adjusted for interim analysis and multiple comparisons.] | (0.74, 1.06)

The second comparison in the same three-arm study, vinorelbine+cisplatin versus docetaxel+carboplatin, did not demonstrate superior survival associated with the docetaxel arm (Kaplan-Meier estimate of median survival was 9.1 months for docetaxel +carboplatin compared to 10.0 months on the vinorelbine+cisplatin arm) and the docetaxel+carboplatin arm did not demonstrate preservation of at least 50% of the survival effect of vinorelbine added to cisplatin. Secondary endpoints evaluated in the trial included objective response and time to progression. There was no statistically significant difference between docetaxel+cisplatin and vinorelbine+cisplatin with respect to objective response and time to progression (see Table 17).

Table 17: Response and TTP Analysis of Docetaxel in Combination Therapy for Chemotherapy-Naive NSCLC
Endpoint | Docetaxel + Cisplatin | Vinorelbine + Cisplatin | p-value
Objective Response Rate | 31.6% | 24.4% | Not Significant
(95% CI) [Adjusted for multiple comparisons.] | (26.5%, 36.8%) | (19.8%, 29.2%)
Median Time to Progression [Kaplan-Meier estimates.] | 21.4 weeks (19.3, 24.6) | 22.1 weeks (18.1, 25.6) | Not Significant
(95% CI)

14.4 Castration-Resistant Prostate Cancer

The safety and efficacy of docetaxel in combination with prednisone in patients with metastatic castration-resistant prostate cancer were evaluated in a randomized multicenter active control trial. A total of 1006 patients with Karnofsky Performance Status (KPS) ≥60 were randomized to the following treatment groups:

- Docetaxel 75 mg/m^2every 3 weeks for 10 cycles.
- Docetaxel 30 mg/m^2administered weekly for the first 5 weeks in a 6-week cycle for 5 cycles.
- Mitoxantrone 12 mg/m^2every 3 weeks for 10 cycles.

All 3 regimens were administered in combination with prednisone 5 mg twice daily, continuously.

In the docetaxel every three week arm, a statistically significant overall survival advantage was demonstrated compared to mitoxantrone. In the docetaxel weekly arm, no overall survival advantage was demonstrated compared to the mitoxantrone control arm. Efficacy results for the docetaxel every 3 week arm versus the control arm are summarized in Table 18 and Figure 5.

Table 18: Efficacy of Docetaxel in the Treatment of Patients with Metastatic Castration-Resistant Prostate Cancer (Intent-to-Treat Analysis)
 | Docetaxel + Prednisone every 3 weeks | Mitoxantrone + Prednisone every 3 weeks
Number of patients | 335 | 337
Median survival (months) | 18.9 | 16.5
95% CI | (17.0-21.2) | (14.4-18.6)
Hazard ratio | 0.761 | --
95% CI | (0.619-0.936) | --
p-value [Stratified log rank test. Threshold for statistical significance = 0.0175 because of 3 arms.] | 0.0094 | --

Figure 5: TAX327 Survival K-M Curves

14.5 Gastric Adenocarcinoma

A multicenter, open-label, randomized trial was conducted to evaluate the safety and efficacy of docetaxel for the treatment of patients with advanced gastric adenocarcinoma, including adenocarcinoma of the gastroesophageal junction, who had not received prior chemotherapy for advanced disease. A total of 445 patients with KPS >70 were treated with either docetaxel (T) (75 mg/m^2on day 1) in combination with cisplatin (C) (75 mg/m^2on day 1) and fluorouracil (F) (750 mg/m^2per day for 5 days) or cisplatin (100 mg/m^2on day 1) and fluorouracil (1000 mg/m^2per day for 5 days). The length of a treatment cycle was 3 weeks for the TCF arm and 4 weeks for the CF arm. The demographic characteristics were balanced between the two treatment arms. The median age was 55 years, 71% were male, 71% were Caucasian, 24% were 65 years of age or older, 19% had a prior curative surgery and 12% had palliative surgery. The median number of cycles administered per patient was 6 (with a range of 1-16) for the TCF arm compared to 4 (with a range of 1-12) for the CF arm. Time to progression (TTP) was the primary endpoint and was defined as time from randomization to disease progression or death from any cause within 12 weeks of the last evaluable tumor assessment or within 12 weeks of the first infusion of study drugs for patients with no evaluable tumor assessment after randomization. The hazard ratio (HR) for TTP was 1.47 (CF/TCF, 95% CI: 1.19-1.83) with a significantly longer TTP (p=0.0004) in the TCF arm. Approximately 75% of patients had died at the time of this analysis. Overall survival was significantly longer (p=0.0201) in the TCF arm with a HR of 1.29 (95% CI: 1.04-1.61). Efficacy results are summarized in Table 19 and Figures 6 and 7.

Table 19: Efficacy of Docetaxel Injection in the Treatment of Patients with Gastric Adenocarcinoma
Endpoint | TCF n=221 | CF n=224
Median TTP (months) | 5.6 | 3.7
(95%CI) | (4.86-5.91) | (3.45-4.47)
Hazard ratio [For the hazard ratio (TCF/CF), values less than 1.00 favor the docetaxel arm.] | 0.68
(95%CI) | (0.55-0.84)
[Unstratified log-rank test] p-value | 0.0004
Median survival (months) | 9.2 | 8.6
(95%CI) | (8.38-10.58) | (7.16-9.46)
Hazard ratio | 0.77
(95%CI) | (0.62-0.96)
p-value | 0.0201
Overall Response Rate (CR+PR) (%) | 36.7 | 25.4
p-value | 0.0106

Subgroup analyses were consistent with the overall results across age, gender and race.

Figure 6: Gastric Cancer Study (TAX325) Time to Progression K-M Curve

Figure 7: Gastric Cancer Study (TAX325) Survival K-M Curve

14.6 Head and Neck Cancer

Induction Chemotherapy Followed by Radiotherapy (TAX323)

The safety and efficacy of docetaxel in the induction treatment of patients with squamous cell carcinoma of the head and neck (SCCHN) was evaluated in a multicenter, open-label, randomized trial (TAX323). In this study, 358 patients with inoperable locally advanced SCCHN, and WHO performance status 0 or 1, were randomized to one of two treatment arms. Patients on the docetaxel arm received docetaxel (T) 75 mg/m^2followed by cisplatin (P) 75 mg/m^2on Day 1, followed by fluorouracil (F) 750 mg/m^2per day as a continuous infusion on Days 1-5. The cycles were repeated every three weeks for 4 cycles. Patients whose disease did not progress received radiotherapy (RT) according to institutional guidelines (TPF/RT). Patients on the comparator arm received cisplatin (P) 100 mg/m^2on Day 1, followed by fluorouracil (F) 1000 mg/m^2/day as a continuous infusion on Days 1-5. The cycles were repeated every three weeks for 4 cycles. Patients whose disease did not progress received RT according to institutional guidelines (PF/RT). At the end of chemotherapy, with a minimal interval of 4 weeks and a maximal interval of 7 weeks, patients whose disease did not progress received radiotherapy (RT) according to institutional guidelines. Locoregional therapy with radiation was delivered either with a conventional fraction regimen (1.8 Gy-2.0 Gy once a day, 5 days per week for a total dose of 66 to 70 Gy) or with an accelerated/hyperfractionated regimen (twice a day, with a minimum interfraction interval of 6 hours, 5 days per week, for a total dose of 70 to 74 Gy, respectively). Surgical resection was allowed following chemotherapy, before or after radiotherapy.

The primary endpoint in this study, progression-free survival (PFS), was significantly longer in the TPF arm compared to the PF arm, p=0.0077 (median PFS: 11.4 vs 8.3 months respectively) with an overall median follow-up time of 33.7 months. Median overall survival with a median follow-up of 51.2 months was also significantly longer in favor of the TPF arm compared to the PF arm (median OS: 18.6 vs 14.2 months respectively). Efficacy results are presented in Table 20 and Figures 8 and 9.

Table 20: Efficacy of Docetaxel in the Induction Treatment of Patients with Inoperable Locally Advanced SCCHN (Intent-to-Treat Analysis)
Endpoint | Docetaxel+ Cisplatin+ Fluorouracil n=177 | Cisplatin+ Fluorouracil n=181
Median progression free survival (months) (95%CI) | 11.4 (10.1-14.0) | 8.3 (7.4-9.1)
Adjusted Hazard ratio (95%CI) [Stratified log-rank test based on primary tumor site] p-value | 0.71 (0.56-0.91) 0.0077
Median survival (months) (95%CI) | 18.6 (15.7-24.0) | 14.2 (11.5-18.7)
Hazard ratio (95%CI) [Stratified log-rank test, not adjusted for multiple comparisons] p-value | 0.71 (0.56-0.90) 0.0055
Best overall response (CR + PR) to chemotherapy (%) (95%CI) | 67.8 (60.4-74.6) | 53.6 (46.0-61.0)
[Chi square test, not adjusted for multiple comparisons] p-value | 0.006
Best overall response (CR + PR) to study treatment [chemotherapy +/- radiotherapy] (%) (95%CI) | 72.3 (65.1-78.8) | 58.6 (51.0-65.8)
p-value | 0.006
A Hazard ratio of less than 1 favors docetaxel+cisplatin+fluorouracil

Figure 8: TAX323 Progression-Free Survival K-M Curve

Figure 9: TAX323 Overall Survival K-M Curve

Induction Chemotherapy Followed by Chemoradiotherapy (TAX324)

The safety and efficacy of docetaxel in the induction treatment of patients with locally advanced (unresectable, low surgical cure, or organ preservation) SCCHN was evaluated in a randomized, multicenter open-label trial (TAX324). In this study, 501 patients, with locally advanced SCCHN, and a WHO performance status of 0 or 1, were randomized to one of two treatment arms. Patients on the docetaxel arm received docetaxel (T) 75 mg/m^2by intravenous infusion on day 1 followed by cisplatin (P) 100 mg/m^2administered as a 30-minute to three-hour intravenous infusion, followed by the continuous intravenous infusion of fluorouracil (F) 1000 mg/m^2/day from day 1 to day 4. The cycles were repeated every 3 weeks for 3 cycles. Patients on the comparator arm received cisplatin (P) 100 mg/m^2as a 30-minute to three-hour intravenous infusion on day 1 followed by the continuous intravenous infusion of fluorouracil (F) 1000 mg/m^2/day from day 1 to day 5. The cycles were repeated every 3 weeks for 3 cycles.

All patients in both treatment arms who did not have progressive disease were to receive 7 weeks of chemoradiotherapy (CRT) following induction chemotherapy 3 to 8 weeks after the start of the last cycle. During radiotherapy, carboplatin (AUC 1.5) was given weekly as a one-hour intravenous infusion for a maximum of 7 doses. Radiation was delivered with megavoltage equipment using once daily fractionation (2 Gy per day, 5 days per week for 7 weeks for a total dose of 70-72 Gy). Surgery on the primary site of disease and/or neck could be considered at any time following completion of CRT.

The primary efficacy endpoint, overall survival (OS), was significantly longer (log-rank test, p=0.0058) with the docetaxel-containing regimen compared to PF (median OS: 70.6 vs 30.1 months respectively, hazard ratio [HR]=0.70, 95% confidence interval [CI]= 0.54-0.90). Overall survival results are presented in Table 21 and Figure 10.

Table 21: Efficacy of Docetaxel in the Induction Treatment Of Patients with Locally Advanced SCCHN (Intent-to-Treat Analysis)
Endpoint | Docetaxel + Cisplatin+ Fluorouracil n=255 | Cisplatin+ Fluorouracil n=246
Median overall survival (months) (95% CI) | 70.6 (49.0-NE) | 30.1 (20.9-51.5)
Hazard ratio: (95% CI) [un-adjusted log-rank test] p-value | 0.70 (0.54-0.90) 0.0058
A Hazard ratio of less than 1 favors docetaxel + cisplatin + fluorouracil

NE - not estimable

Figure 10: TAX324 Overall Survival K-M Curve

15 REFERENCES

1. “OSHA Hazardous Drugs.” http://www.osha.gov/SLTC/hazardousdrugs/index.html

16 HOW SUPPLIED/STORAGE AND HANDLING

16.1 How Supplied

One-vial Docetaxel Injection

Docetaxel Injection is supplied in multiple-dose (20 mg/mL, 80 mg/4 mL and 160 mg/8 mL) vials as a sterile, pyrogen-free, non-aqueous solution.

Docetaxel Injection Multiple-Dose Vials

Docetaxel Injection 160 mg/8 mL: The vial is in one carton. NDC 16729-267-65

Docetaxel Injection 80 mg/4 mL: The vial is in one carton. NDC 16729-267-64

Docetaxel Injection 20 mg/mL: The vial is in one carton. NDC 16729-267-63

16.2 Storage

Store between 15°C and 25°C (59°F and 77°F). Retain in the original package to protect from light. Freezing does not adversely affect the product.

After initial puncture, Docetaxel Injection multiple dose vials are stable for 28 days when stored at room temperature, with protection from light.

16.3 Handling and Disposal

Docetaxel Injection is a hazardous drug. Follow applicable special handling and disposal procedures. ¹

17 PATIENT COUNSELING INFORMATION

Advise the patient to read the FDA-approved patient labeling (Patient Information).

Bone Marrow Suppression

Advise patients that periodic assessment of their blood count will be performed to detect neutropenia, thrombocytopenia, and/ or anemia [see Contraindications (4), Warnings and Precautions (5.3)]. Instruct patients to monitor their temperature frequently and immediately report any occurrence of fever.

Enterocolitis and Neutropenic Colitis

Advise patients of the symptoms of colitis, such as abdominal pain or tenderness, and/or diarrhea, with or without fever, and instruct patients to promptly contact their healthcare provider if they experience these symptoms [see Dosage and Administration (2.7)and Warnings and Precautions (5.4)].

Hypersensitivity Reactions

Ask patients whether they have previously received paclitaxel therapy, and if they have experienced a hypersensitivity reaction to paclitaxel. Instruct patients to immediately report to their healthcare provider signs of a hypersensitivity reaction [see Contraindications (4), Warnings and Precautions (5.5)].

Fluid Retention

Advise patients to report signs of fluid retention such as peripheral edema in the lower extremities, weight gain, and dyspnea immediately to their healthcare provider [see Warnings and Precautions (5.6)].

Second Primary Malignancies

Advise patients on the risk of second primary malignancies during treatment with Docetaxel Injection [see Warnings and Precautions (5.7)].

Cutaneous Reactions

Advise patients that localized erythema of the extremities and severe skin toxicities may occur. Instruct patients to immediately report severe cutaneous reactions to their healthcare provider [see Dosage and Administration (2.7)and Warnings and Precautions (5.8)].

Neurologic Reactions

Advise patients that neurosensory symptoms or peripheral neuropathy may occur. Instruct patients to immediately report neurologic reactions to their healthcare provider [see Dosage and Administration (2.7)and Warnings and Precautions (5.9)].

Eye Disorders

Advise patients that vision disturbances and excessive tearing are associated with Docetaxel Injection administration. Instruct patients to immediately report any vision changes to their healthcare provider [see Warnings and Precautions (5.10)] .

Gastrointestinal Reactions

Explain to patients that nausea, vomiting, diarrhea, and constipation are associated with Docetaxel Injection administration. Instruct patients to report any severe events to their healthcare provider [see Adverse Reactions (6)] .

Cardiac Disorders

Advise patients to report any irregular and/or rapid heartbeat, severe shortness of breath, dizziness, and/or fainting immediately to their healthcare provider [see Adverse Reactions (6)] .

Other Common Adverse Reactions

Advise patients that other common adverse reactions associated with Docetaxel Injection may include alopecia (cases of permanent hair loss have been reported), asthenia, anorexia, dysgeusia, mucositis, myalgia, nail disorders, or pain. Instruct patients to report these reactions to their healthcare provider if serious events occur [see Adverse Reactions (6)] .

Importance of Corticosteroids

Explain the significance of oral corticosteroids such as dexamethasone administration to the patient to help facilitate compliance. Instruct patients to report to their healthcare provider if they were not compliant with the oral corticosteroid regimen [see Dosage and Administration (2.6)] ].

Embryo-Fetal Toxicity

Docetaxel can cause fetal harm. Advise patients to inform their healthcare provider of a known or suspected pregnancy. Advise patients to avoid becoming pregnant while receiving this drug. Advise female patients of reproductive potential to use effective contraceptives during treatment and for 2 months after the last dose of docetaxel. Advise male patients with female partners of reproductive potential to use effective contraception during treatment and for 4 months after the last dose of docetaxel [see Warnings and Precautions (5.12), and Use in Specific Populations (8.1, 8.3)].

Lactation

Advise women not to breastfeed during docetaxel treatment and for 1 week after the last dose [see Use in Specific Populations (8.2)] .

Infertility

Advise males of reproductive potential that docetaxel may impair fertility [see Nonclinical Toxicology (13.1)] .

Alcohol Content in Docetaxel Injection

Explain to patients the possible effects of the alcohol content in docetaxel, including possible effects on the central nervous system [see Warnings and Precautions (5.13)] .

Tumor Lysis Syndrome

Advise patients of the potential risk of tumor lysis syndrome and to immediately report any signs or symptoms associated with this event (nausea, vomiting, confusion, shortness of breath, seizure, irregular heartbeat, dark or cloudy urine, reduced amount of urine, unusual tiredness, muscle cramps) to their healthcare provider. Advise patients of the importance of keeping scheduled appointment for blood work or other laboratory tests and of drinking adequate fluids to avoid dehydration. [see Warnings and Precautions (5.14)] .

Ability to Drive or Operate Machines

Explain to patients that docetaxel may impair their ability to drive or operate machines due to its side effects [see Adverse Reactions (6)] or due to the alcohol content of docetaxel [see Warnings and Precautions (5.13)] . Advise them not to drive or use machines if they experience these side effects during treatment.

Drug Interactions

Inform patients about the risk of drug interactions and the importance of providing a list of prescription and non-prescription drugs to their healthcare provider [see Drug Interactions (7)] .

Manufactured For:
Accord Healthcare, Inc.,
8041 Arco Corporate Drive Suite 200 Raleigh, NC
27617, USA.

Manufactured By:Intas Pharmaceuticals Limited,
Ahmedabad – 380 054,
India.

10 0739 4 6023402

Revised September 2023

Patient Information
Docetaxel (doe-se-TAKS-el) Injection
for intravenous use

What is the most important information I should know about Docetaxel Injection?
Docetaxel Injection can cause serious side effects, including death.

- The chance of death in people who receive Docetaxel Injection is higher if you:
  - have liver problems
  - receive high doses of Docetaxel Injection
  - have non-small cell lung cancer and have been treated with chemotherapy medicines that contain platinum
- Docetaxel Injection can affect your blood cells.Your healthcare provider should do routine blood tests during treatment with Docetaxel Injection. This will include regular checks of your white blood cell counts. If your white blood cells are too low, your healthcare provider may not treat you with Docetaxel Injection until you have enough white blood cells. People with low white blood cell counts can develop life-threatening infections. The earliest sign of infection may be fever. Follow your healthcare provider’s instructions for how often to take your temperature during treatment with Docetaxel Injection. Call your healthcare provider right away if you have a fever.
- Swelling (inflammation) of the small intestine and colon.This can happen at any time during treatment and could lead to death as early as the first day you get symptoms. Tell your healthcare provider right away if you develop new or worse symptoms of intestinal problems, including stomach (abdominal) pain or tenderness or diarrhea, with or without fever.
- Severe allergic reactionsare medical emergencies that can happen in people who receive Docetaxel Injection and can lead to death. You may be at higher risk of developing a severe allergic reaction to Docetaxel Injection if you are allergic to paclitaxel. Your healthcare provider will monitor you closely for allergic reactions during your Docetaxel Injection infusion.
  Tell your healthcare provider right away if you have any of these signs of a severe allergic reaction:
  - trouble breathing
  - sudden swelling of your face, lips, tongue, throat, or trouble swallowing
  - hives (raised bumps), rash, or redness all over your body
- Your body may hold too much fluid (severe fluid retention)during treatment with Docetaxel Injection. This can be life threatening. To decrease the chance of this happening, you must take another medicine, a corticosteroid, before each Docetaxel Injection treatment. You must take the corticosteroid exactly as your healthcare provider tells you. Tell your healthcare provider or nurse before your Docetaxel Injection treatment if you forgot to take your corticosteroid dose or do not take it as your healthcare provider tells you. Tell your healthcare provider right away if you have swelling in your legs or feet, weight gain or shortness of breath.
- Risk of new cancers.An increase in new (second) cancers has happened in people treated with Docetaxel Injection together with certain other anticancer treatments. This includes certain blood cancers, such as acute myeloid leukemia (AML), myelodysplastic syndrome (MDS), non-Hodgkin’s Lymphoma (NHL), and kidney cancer.
  - Changes in blood counts due to leukemia and other blood disorders may occur years after treatment with Docetaxel Injection.
  Your healthcare provider will check you for new cancers during and after your treatment with Docetaxel Injection.
- Severe skin problems.
  Tell your healthcare provider right away if you have any of these signs of a severe skin reaction:
  - redness and swelling of your arms and legs.
  - blistering, peeling or bleeding on any part of your skin (including your lips, eyes, mouth, nose, genitals, hands or feet) with or without a rash. You may also have flu-like symptoms such as fever, chills, or muscle aches.
  - red, scaly rash all over your body with blisters small red or white bumps under the skin that contain pus (pustules) and fever

What is Docetaxel Injection?
Docetaxel Injection is a prescription anticancer medicine used to treat certain people with:

- breast cancer
- non-small cell lung cancer
- prostate cancer
- stomach cancer
- head and neck cancer

It is not known if Docetaxel Injection is effective in children.

Do not receive Docetaxel Injection if you:

- have a low white blood cell count.
- have had a severe allergic reaction to:
  - docetaxel, the active ingredient in Docetaxel Injection, or
  - any other medicines that contain polysorbate 80. Ask your healthcare provider or pharmacist if you are not sure.
  See “What is the most important information I should know about Docetaxel Injection?”for the signs and symptoms of a severe allergic reaction. See the end of this Patient Information for a complete list of the ingredients in Docetaxel Injection.

Before you receive Docetaxel Injection, tell your healthcare provider about all of your medical conditions, including if you:

- are allergic to any medicines, including paclitaxel. See “Do not receive Docetaxel Injection if you”.
- have liver problems
- have kidney problems
- are pregnant or plan to become pregnant. Docetaxel Injection can harm your unborn baby. You should not become pregnant during treatment with Docetaxel Injection. Tell your healthcare provider if you become pregnant or you think you may be pregnant during treatment with Docetaxel Injection.
  Females who are able to become pregnant:
  - Your healthcare provider will check to see if you are pregnant before you start treatment with Docetaxel Injection.
  - You should use effective birth control (contraception) during treatment with Docetaxel Injection and for 4 months after the last dose.
  Maleswith female partners who are able to become pregnant should use effective birth control during treatment with Docetaxel Injection and for 4 months after the last dose.
  Talk to your healthcare provider if you have questions about birth control options that are right for you.
- are breastfeeding or plan to breastfeed. It is not known if Docetaxel Injection passes into your breast milk. Do not breastfeed during treatment with Docetaxel Injection and for 1 week after the last dose.

Tell your healthcare provider about all the medicines you take,including prescription and over-the-counter medicines, vitamins, and herbal supplements. Docetaxel Injection may affect the way other medicines work, and other medicines may affect the way Docetaxel Injection works.
Know the medicines you take. Keep a list of them to show your healthcare provider and pharmacist when you get a new medicine.

How will I receive Docetaxel Injection?

- Docetaxel Injection will be given to you as an intravenous (IV) injection into your vein, usually over 1 hour.
- Docetaxel Injection is usually given every 3 weeks.
- Your healthcare provider will decide how long you will receive treatment with Docetaxel Injection.
- Your healthcare provider will check your blood cell counts and other blood tests during your treatment with Docetaxel Injection to check for side effects of Docetaxel Injection.
- Your healthcare provider may stop your treatment, change the timing of your treatment, or change the dose of your treatment if you have certain side effects while receiving Docetaxel Injection.

What are the possible side effects of Docetaxel Injection?
Docetaxel Injection may cause serious side effects including death.

- See “ What is the most important information I should know about Docetaxel Injection?”
- Neurologic problems.Neurologic symptoms are common in people who receive Docetaxel Injection but can be severe. Tell your healthcare provider right away if you have numbness, tingling, or burning in your hands or feet (peripheral neuropathy) or weakness of your legs, feet, arms, or hands (motor weakness).
- Vision problemsincluding blurred vision or loss of vision. Tell your healthcare provider right away if you have any vision changes.
- Docetaxel Injection contains alcohol.The alcohol content in Docetaxel Injection may impair your ability to drive or use machinery right after receiving Docetaxel Injection. Consider whether you should drive, operate machinery or do other dangerous activities right after you receive Docetaxel Injection treatment.
- Tumor lysis syndrome (TLS).TLS is caused by the fast breakdown of cancer cells. TLS can cause kidney failure, the need for dialysis treatment, or heart problems, and may lead to death. Your healthcare provider will do blood tests to check for TLS when you first start treatment and during treatment with Docetaxel Injection. Tell your healthcare provider right away if you have any symptoms of TLS during treatment with Docetaxel Injection, including:
  - nausea
  - irregular heartbeat
  - vomiting
  - dark or cloudy urine
  - confusion
  - reduced amount of urine
  - shortness of breath
  - unusual tiredness
  - muscle cramps
- You may experience side effects of Docetaxel Injection that may impair your ability to drive, use tools, or operate machines. If this happens, do not drive or use any tools or machines before discussing with your healthcare provider.

The most common side effects of Docetaxel Injection include:

- infections
- low white blood cells (help fight infections),
  low red blood cells (anemia) and low platelets (help blood to clot)
- allergic reactions
  (See “What is the most important information I should know about Docetaxel Injection?”)
- changes in your sense of taste
- shortness of breath
- constipation
- decreased appetite
- changes in your fingernails or toenails
- swelling of your hands, face or feet

- feeling weak or tired
- joint and muscle pain
- nausea and vomiting
- diarrhea
- mouth or lip sores
- hair loss: in some people, permanent hair loss has been reported
- redness of the eye, excess tearing
- skin reactions at the site of Docetaxel Injection administration such as increased skin pigmentation, redness, tenderness, swelling, warmth or dryness of the skin
- tissue damage if Docetaxel Injection leaks out of the vein into the tissues

Tell your healthcare provider if you have a fast or irregular heartbeat, severe shortness of breath, dizziness or fainting during your infusion. If any of these events occurs after your infusion, get medical help right away.
Docetaxel Injection may affect fertility in males. Talk to your healthcare provider if this is a concern for you.
These are not all of the possible side effects of Docetaxel Injection. For more information, ask your healthcare provider or pharmacist.
Call your healthcare provider for medical advice about side effects. You may report side effects to FDA at 1-800-FDA1088.

General information about the safe and effective use of Docetaxel Injection
Medicines are sometimes prescribed for purposes other than those listed in this Patient Information. You can ask your pharmacist or healthcare provider for information about Docetaxel Injection that is written for health professionals.

What are the ingredients in Docetaxel Injection?

Active ingredient:docetaxel anhydrous USP

Inactive ingredients:anhydrous citric acid for pH adjustment, polysorbate 80 and dehydrated alcohol solution

Manufactured For:Accord Healthcare, Inc.,
8041 Arco Corporate Drive Suite 200 Raleigh, NC 27617, USA.

Manufactured By:Intas Pharmaceuticals Limited, Ahmedabad – 380 054, India. For more information call 1-866-941-7875

This Patient Information has been approved by the U.S. Food and Drug Administration.

Revised:September 2023

Every three-week injection of Docetaxel Injection for breast, non-small cell lung and stomach, and head and neck cancers

Take your oral corticosteroid medicine as your healthcare provider tells you.

Oral corticosteroid dosing:

Day 1Date:________ Time:_____ AM______ PM

Day 2Date:________ Time:_____ AM______ PM

(Docetaxel Injection Treatment Day)

Day 3Date:________ Time:_____ AM______ PM

Every three-week injection of Docetaxel Injection for prostate cancer
Take your oral corticosteroid medicine as your healthcare provider tells you.

Oral corticosteroiddosing:

Date:________ Time:_____

Date:________ Time:_____

(Docetaxel Injection Treatment Day)

Time:_____

PACKAGE LABEL-PRINCIPAL DISPLAY PANEL - Carton 160 mg/8 mL

NDC 16729- 267-65

Docetaxel Injection 160 mg/8 mL

Rx Only

160 mg/8 mL

PACKAGE LABEL-PRINCIPAL DISPLAY PANEL - Label 160 mg/8 mL

NDC 16729- 267-65

Docetaxel Injection 160 mg/8 mL

Rx Only

160 mg/8 mL

PACKAGE LABEL-PRINCIPAL DISPLAY PANEL - Carton 80 mg/4 mL

NDC 16729- 267-64

Docetaxel Injection 80 mg/4 mL

Rx Only

80 mg/4 mL

PACKAGE LABEL-PRINCIPAL DISPLAY PANEL - Label 80 mg/4 mL

NDC 16729- 267-64

Docetaxel Injection 80 mg/4 mL

Rx Only

80 mg/4 mL

PACKAGE LABEL-PRINCIPAL DISPLAY PANEL - Carton 20 mg/mL

NDC 16729- 267-63

Docetaxel Injection 20 mg/mL

Rx Only

20 mg/mL

PACKAGE LABEL-PRINCIPAL DISPLAY PANEL - Label 20 mg/mL

DC 16729- 267-63

Docetaxel Injection 20 mg/mL

Rx Only

20 mg/mL